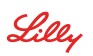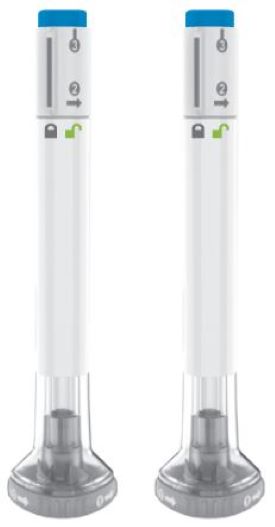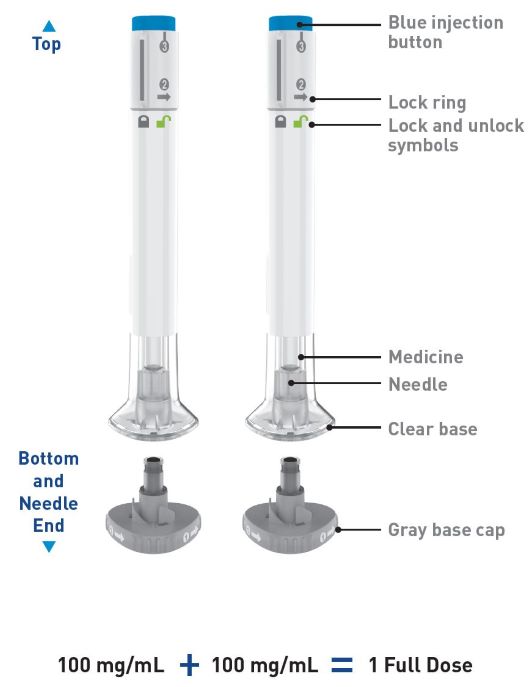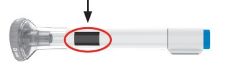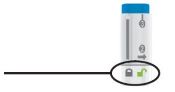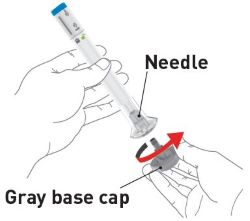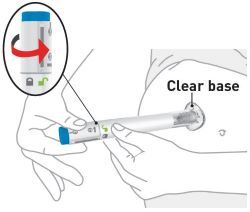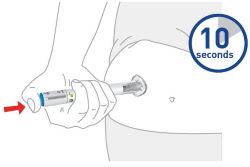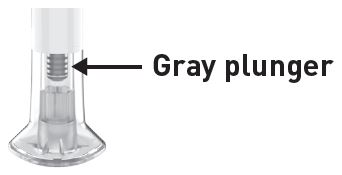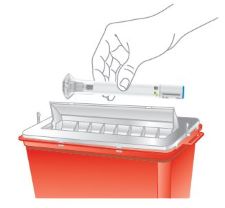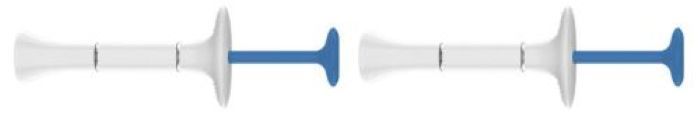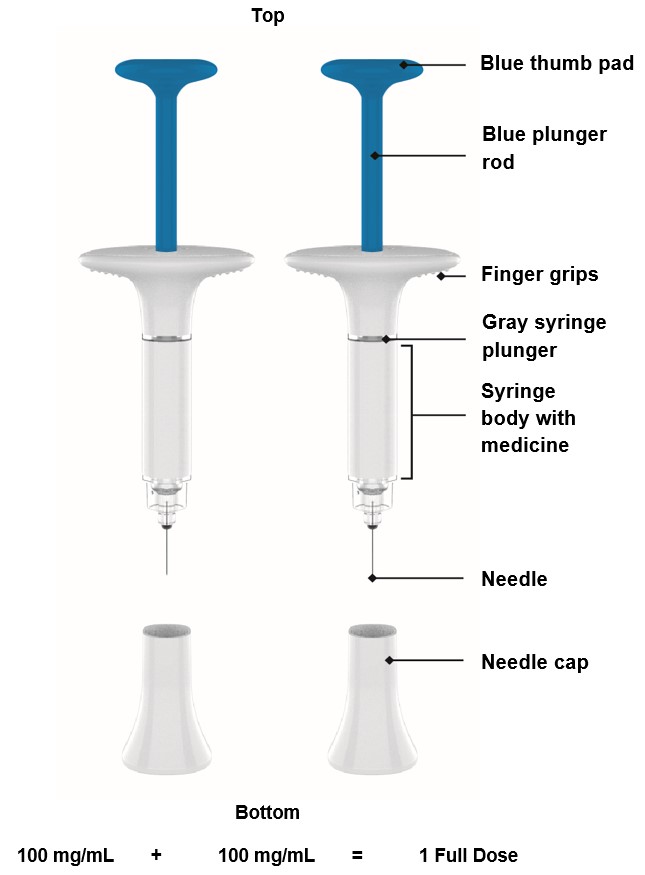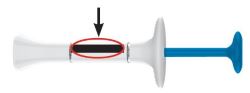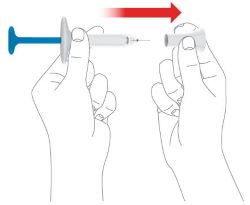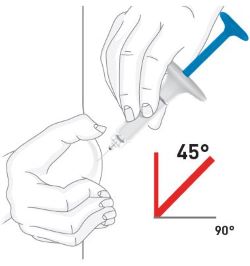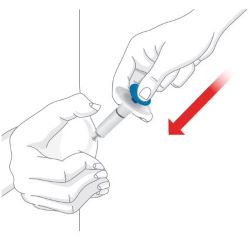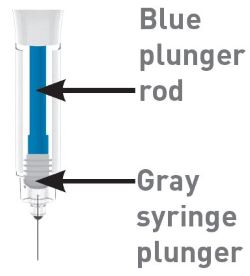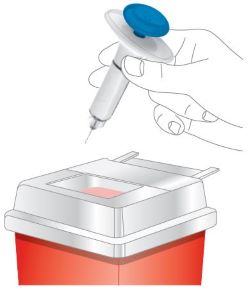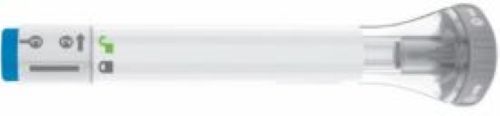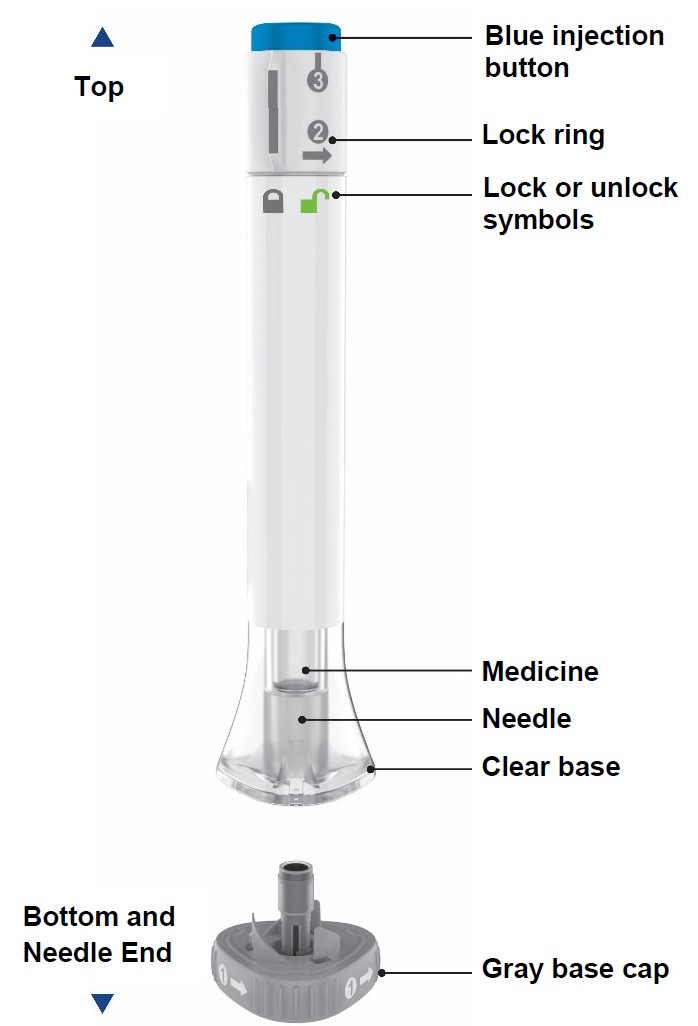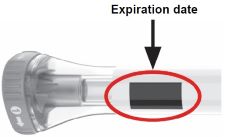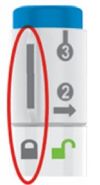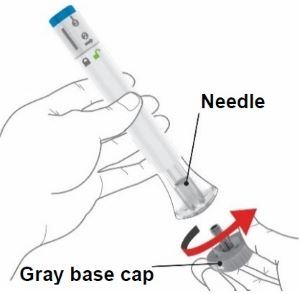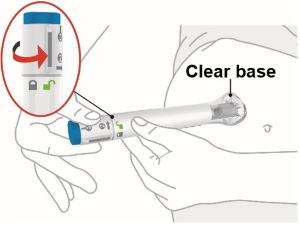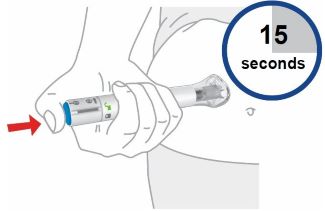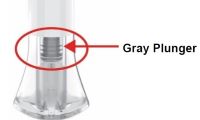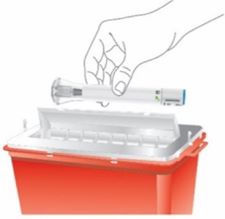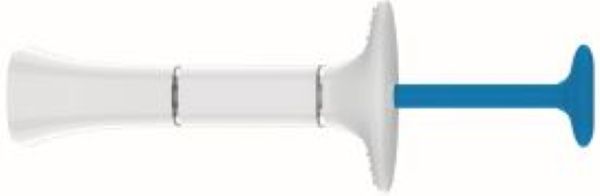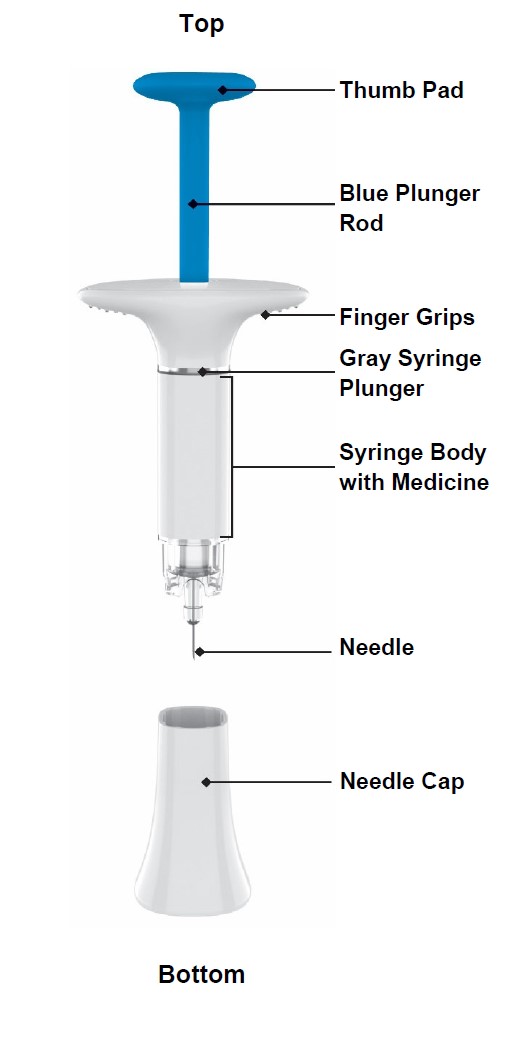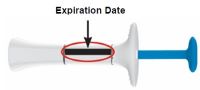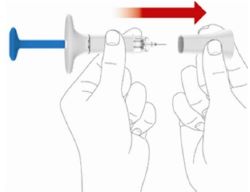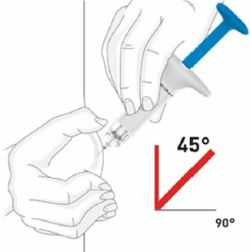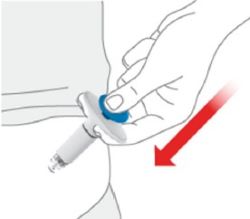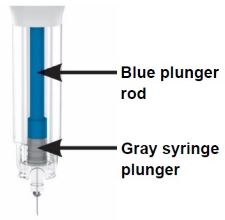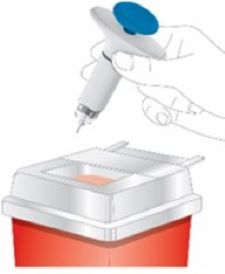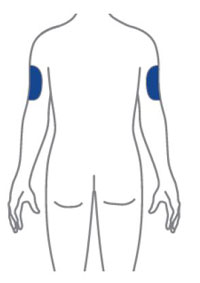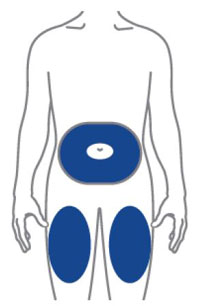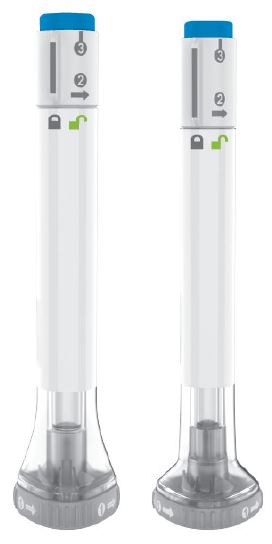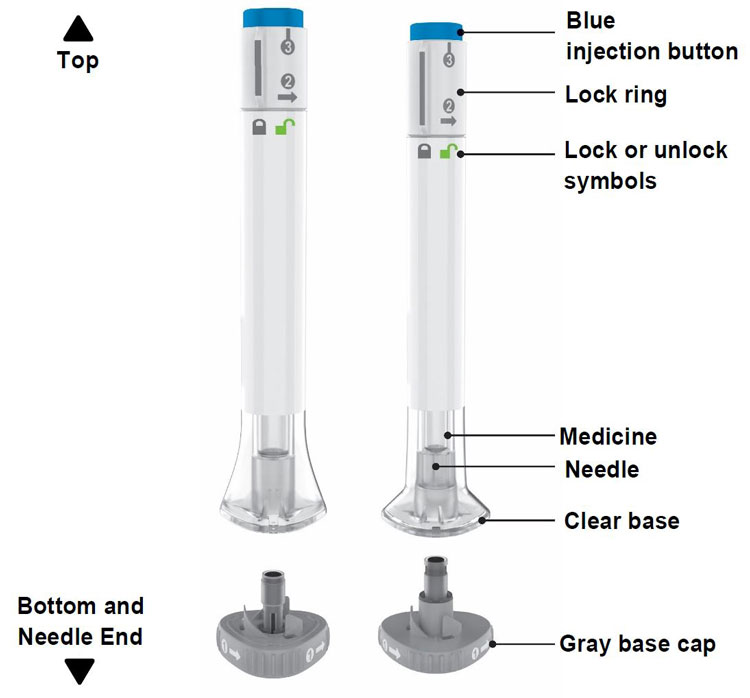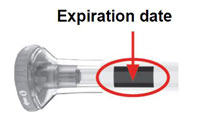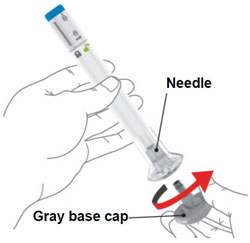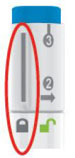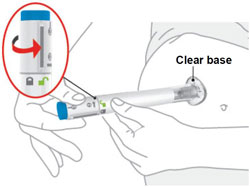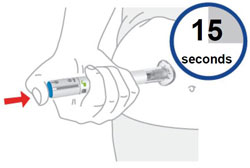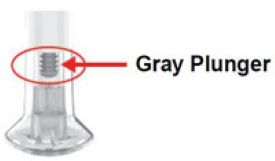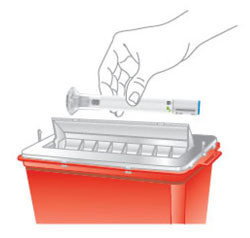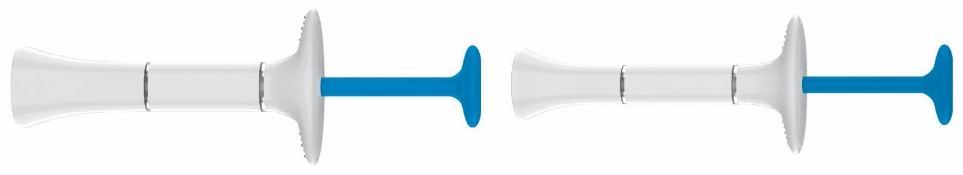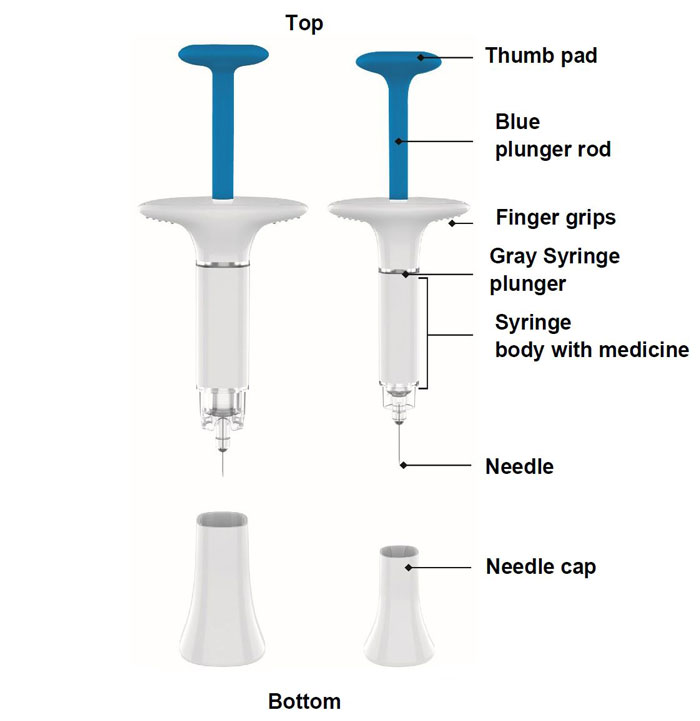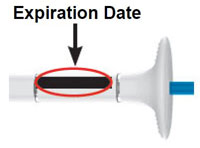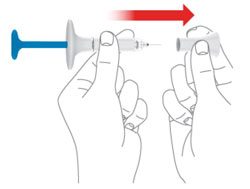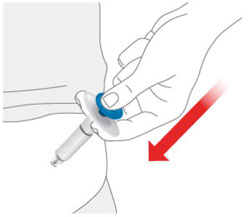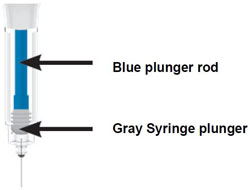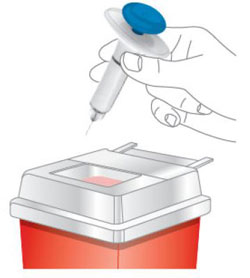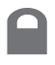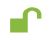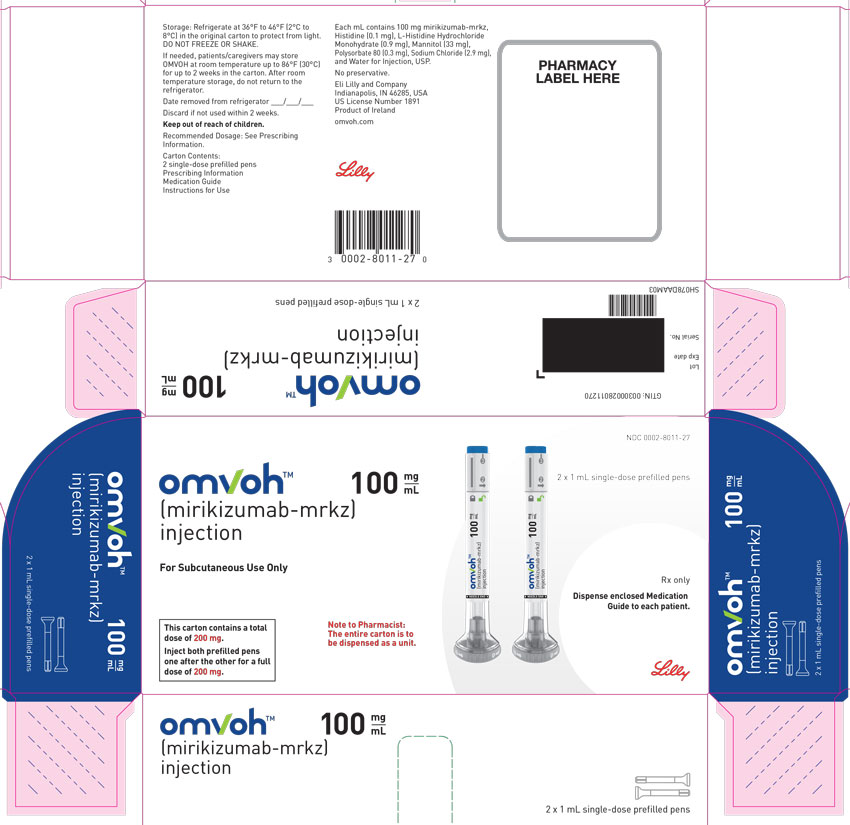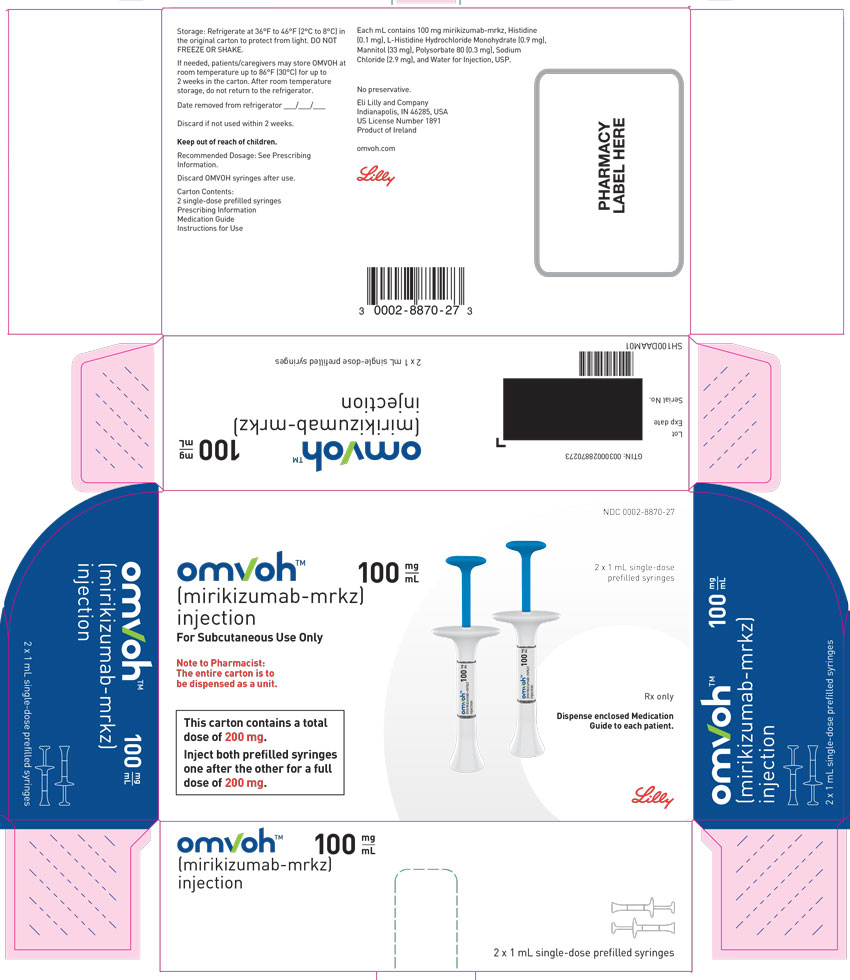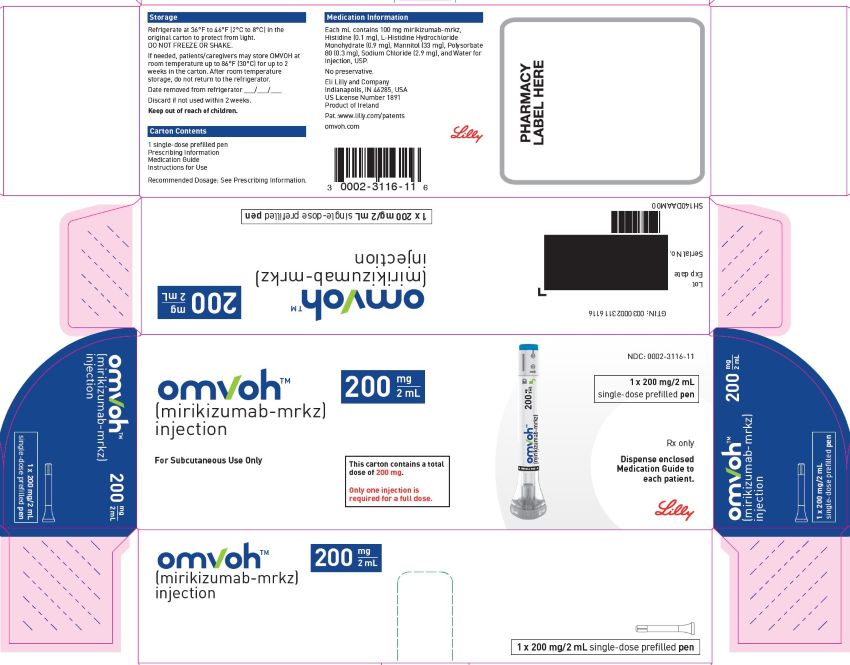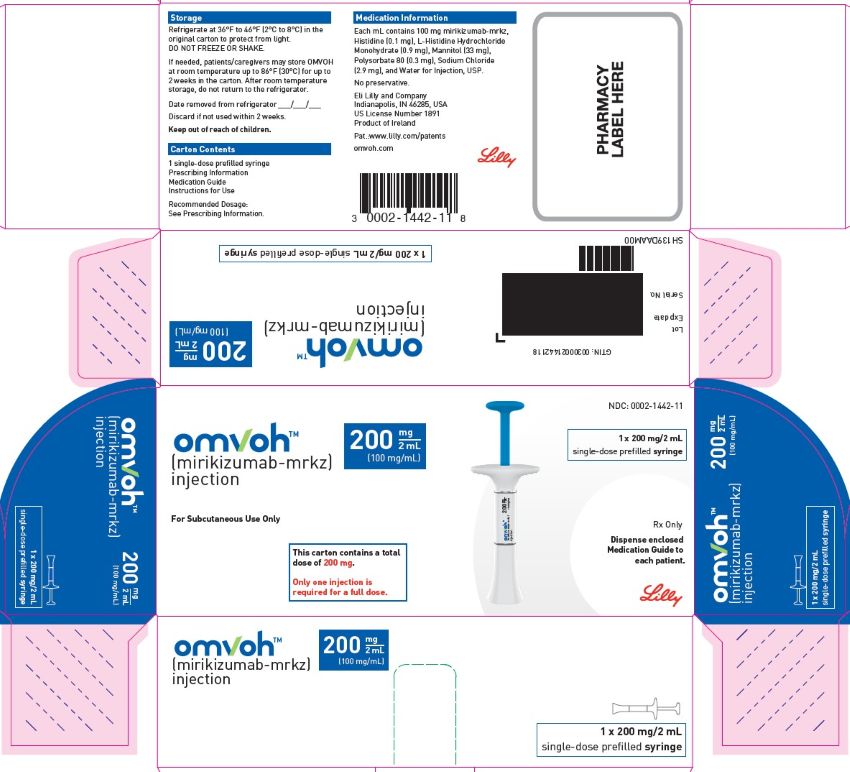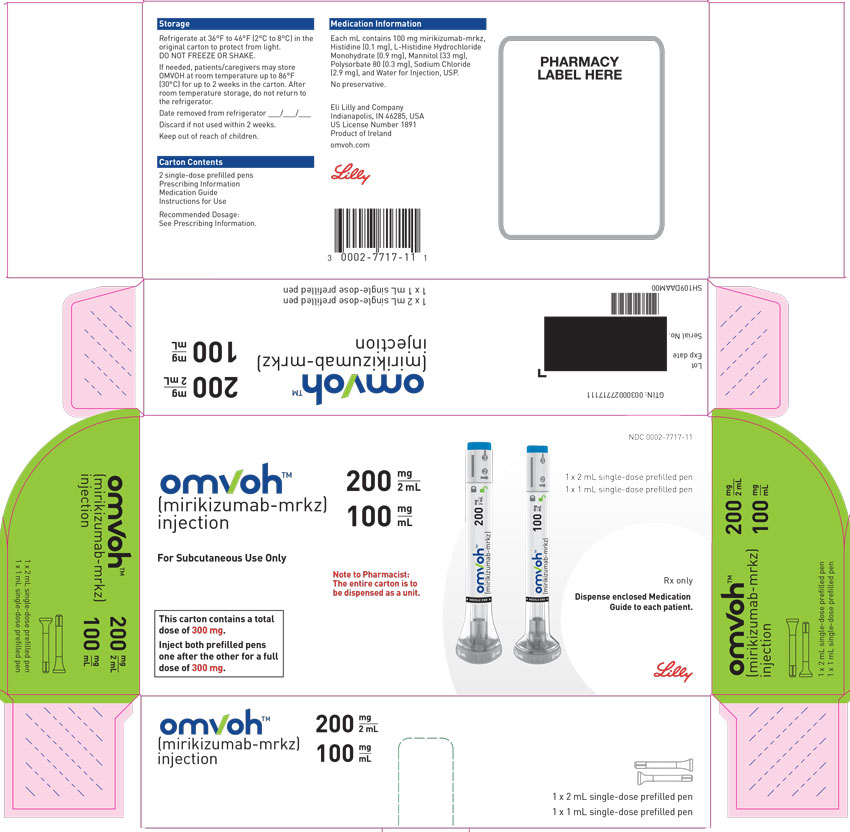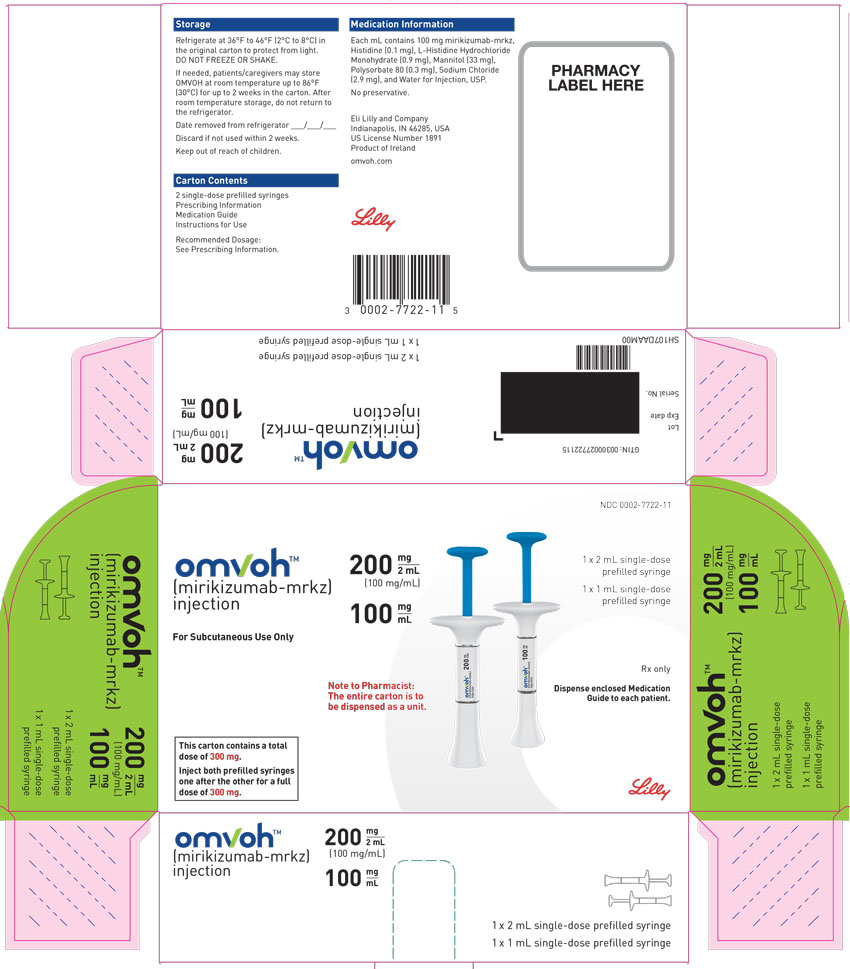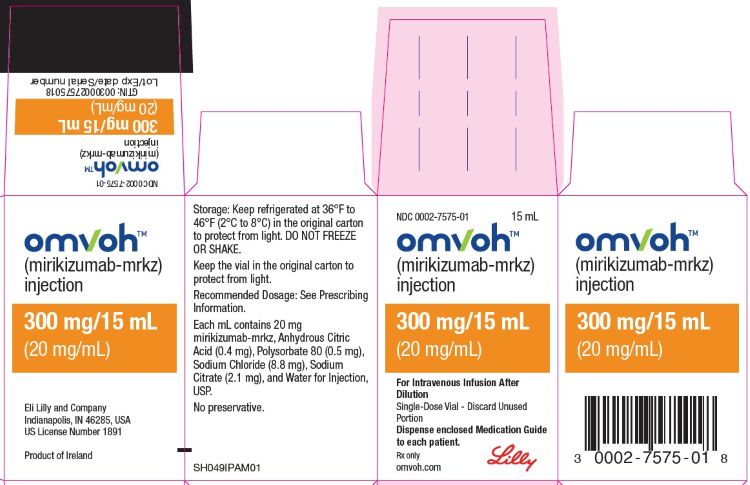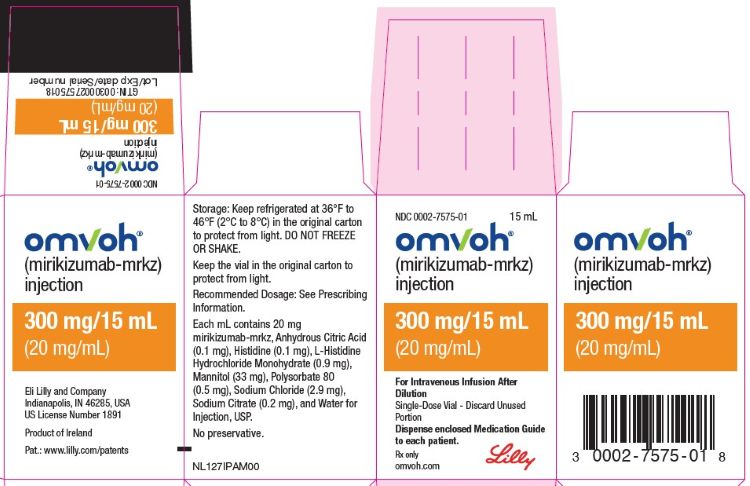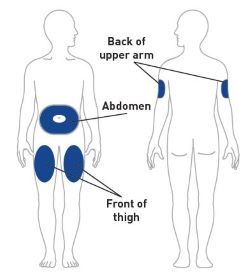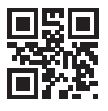 DRUG LABEL: Omvoh
NDC: 0002-7575 | Form: INJECTION, SOLUTION
Manufacturer: Eli Lilly and Company
Category: prescription | Type: HUMAN PRESCRIPTION DRUG LABEL
Date: 20251104

ACTIVE INGREDIENTS: mirikizumab 20 mg/1 mL
INACTIVE INGREDIENTS: trisodium citrate dihydrate; anhydrous citric acid; sodium chloride; polysorbate 80; water

HIGHLIGHTS OF PRESCRIBING INFORMATION

These highlights do not include all the information needed to use OMVOH safely and effectively. See full prescribing information for OMVOH.
OMVOH (mirikizumab-mrkz) injection, for intravenous or subcutaneous use
Initial U.S. Approval: 2023

RECENT MAJOR CHANGES

Indications and Usage (1) |  | 1/2025
Dosage and Administration
 | Recommended Dosage for Ulcerative Colitis (2.2) | 10/2025
 | Recommended Dosage for Crohn's Disease (2.3) | 1/2025
 | Preparation and Administration Instructions for Intravenous Infusion (2.4) | 1/2025
 | Preparation and Administration Instructions for Subcutaneous Injection(2.5) | 10/2025

1 INDICATIONS AND USAGE

OMVOHTM is an interleukin-23 antagonist indicated for the treatment of:

- moderately to severely active ulcerative colitis in adults (1)
- moderately to severely active Crohn's disease in adults (1)

2 DOSAGE AND ADMINISTRATION

Prior to Treatment Initiation

- Evaluate patients for tuberculosis (TB) infection. (2.1, 5.3)
- Obtain liver enzymes and bilirubin levels. (2.1, 5.4)
- Complete all age-appropriate vaccinations according to current immunization guidelines. (2.1, 5.5)

Recommended Dosage for Ulcerative Colitis

- Induction Dosage: Week 0, Week 4, and Week 8: Infuse 300 mg intravenously over at least 30 minutes. (2.2)
- Maintenance Dosage: Week 12 and every 4 weeks thereafter: Inject 200 mg subcutaneously (given as either one injection of 200 mg or as two consecutive injections of 100 mg each). (2.2)

Recommended Dosage for Crohn's Disease

- Induction Dosage: Week 0, Week 4, and Week 8: Infuse 900 mg intravenously over at least 90 minutes. (2.3)
- Maintenance Dosage: Week 12 and every 4 weeks thereafter: Inject 300 mg subcutaneously (given as two consecutive injections of 100 mg and 200 mg in any order). (2.3)

Preparation and Administration Instructions

- See the full prescribing information for preparation, administration and storage information for intravenous infusion and subcutaneous injection. (2.2, 2.3, 2.4, 2.5)

3 DOSAGE FORMS AND STRENGTHS

Intravenous Infusion (3)

- Injection: 300 mg/15 mL (20 mg/mL) solution in a single-dose vial

Subcutaneous Injection (3):

- Injection: 100 mg/mL solution in a single-dose prefilled pen
- Injection: 100 mg/mL solution in a single-dose prefilled syringe
- Injection: 200 mg/2 mL solution in a single-dose prefilled pen
- Injection: 200 mg/2 mL (100 mg/mL) solution in a single-dose prefilled syringe

4 CONTRAINDICATIONS

History of serious hypersensitivity reaction to mirikizumab-mrkz or any of the excipients. (4, 5.1).

5 WARNINGS AND PRECAUTIONS

- Hypersensitivity Reactions: Serious hypersensitivity reactions, including anaphylaxis and infusion-related reactions, have been reported. If a severe hypersensitivity reaction occurs, discontinue and initiate appropriate treatment. (5.1)
- Infections: OMVOH may increase the risk of infection. Do not initiate treatment with OMVOH in patients with a clinically important active infection until the infection resolves or is adequately treated. If a serious infection develops, do not administer OMVOH until the infection resolves. (5.2)
- Tuberculosis: Do not administer OMVOH to patients with active TB infection. Monitor patients receiving OMVOH for signs and symptoms of active TB during and after treatment. (5.3)
- Hepatotoxicity: Drug-induced liver injury has been reported. Monitor liver enzymes and bilirubin levels at baseline and for at least 24 weeks of treatment and thereafter according to routine patient management. Interrupt treatment if drug-induced liver injury is suspected, until this diagnosis is excluded. (5.4)
- Immunizations: Avoid use of live vaccines. (5.5)

6 ADVERSE REACTIONS

Most common adverse reactions are:

- Ulcerative colitis (≥2%):
  - Induction: upper respiratory tract infections and arthralgia. (6.1)
  - Maintenance: upper respiratory tract infections, injection site reactions, arthralgia, rash, headache, and herpes viral infection. (6.1)
- Crohn's disease (≥5%): upper respiratory tract infections, injection site reactions, headache, arthralgia, and elevated liver tests (6.1)

To report SUSPECTED ADVERSE REACTIONS, contact Eli Lilly and Company at 1-800-LillyRx (1-800-545-5979) or FDA at 1-800-FDA-1088 or www.fda.gov/medwatch.

FULL PRESCRIBING INFORMATION

1 INDICATIONS AND USAGE

OMVOH is indicated for the treatment of:

- moderately to severely active ulcerative colitis in adults.
- moderately to severely active Crohn's disease in adults.

2 DOSAGE AND ADMINISTRATION

2.1 Recommended Evaluations and Immunizations Prior to Treatment Initiation

- Evaluate patients for tuberculosis (TB) infection prior to initiating treatment with OMVOH [see Warnings and Precautions (5.3)].
- Obtain liver enzymes and bilirubin levels prior to initiating treatment with OMVOH [see Warnings and Precautions (5.4)].
- Complete all age-appropriate vaccinations according to current immunization guidelines [see Warnings and Precautions (5.5)].

2.2 Recommended Dosage for Ulcerative Colitis

Induction Dosage

Week 0, Week 4, and Week 8: Infuse 300 mg intravenously over at least 30 minutes [see Dosage and Administration (2.4)].

Maintenance Dosage

Week 12 and every 4 weeks thereafter: Inject 200 mg subcutaneously (given as one injection of 200 mg or as two consecutive injections of 100 mg each) [see Dosage and Administration (2.5) and How Supplied/Storage and Handling (16)].

2.3 Recommended Dosage for Crohn's Disease

Induction Dosage

Week 0, Week 4, and Week 8: Infuse 900 mg intravenously over at least 90 minutes [see Dosage and Administration (2.4)].

Maintenance Dosage

Week 12 and every 4 weeks thereafter: Inject 300 mg subcutaneously (given as two consecutive injections of 100 mg and 200 mg in any order) [see Dosage and Administration (2.5) and How Supplied/Storage and Handling (16)].

2.4 Preparation and Administration Instructions for Intravenous Infusion

1. OMVOH for intravenous use is intended for administration by a healthcare provider using aseptic technique.
2. Parenteral drug products should be inspected visually for particulate matter and discoloration prior to administration, whenever solution and container permit. The solution should be a clear to opalescent, colorless to slightly yellow to slightly brown solution, and free of visible particles. Do not use OMVOH if it is cloudy or there are visible particles.
3. Prior to intravenous administration, determine the dose needed based on the patient's indication (see Table 1 below). For Crohn's disease, discard 45 mL of the infusion bag prior to adding vial contents. Withdraw the required amount of solution from the vial(s) using a 18 gauge to 21 gauge needle and transfer to an infusion bag containing 0.9% Sodium Chloride Injection or 5% Dextrose Injection (see Table 1 below). Do not mix with other drugs. Do not dilute or infuse through the same intravenous line with other solutions.
  Table 1: Intravenous Induction Dose and Volume of Diluent Required
  Indication | Intravenous Induction Dose | Number of OMVOH 300mg/15mL vials needed | Volume of 0.9% Sodium Chloride or 5% Dextrose Injection
  Ulcerative colitis | 300 mg | 1 | 50 mL, 100 mL, or 250 mL
  Crohn's disease | 900 mg | 3 | 100 mL or 250 mL
4. Gently invert the infusion bag to mix the contents. Do not shake the prepared infusion bag.
5. Connect the intravenous administration set (infusion line) to the prepared infusion bag and prime the line.
6. Infuse the diluted solution intravenously over a period of at least 30 minutes for the 300 mg dose; at least 90 minutes for the 900 mg dose. If stored refrigerated, allow the diluted solution in the infusion bag to warm to room temperature prior to the start of the intravenous infusion.
7. At the end of the infusion, flush the line with 0.9% Sodium Chloride Injection or 5% Dextrose Injection.
  - Administer the flush at the same infusion rate as used for OMVOH administration.
  - The time required to flush OMVOH solution from the infusion line is in addition to the minimum 30-minute infusion time.

Storage of Diluted Solution

- Start the infusion immediately after preparation. If not used immediately, store the diluted infusion solution in the refrigerator at 2°C to 8°C (36°F to 46°F). Use the diluted infusion solution within 48 total hours, of which not more than 5 hours are permitted at non-refrigerated temperatures not to exceed 25°C (77°F), starting from the time of vial puncture.
- Keep drug product away from direct heat or light. Do not freeze the diluted solution in the prepared infusion bag.

2.5 Preparation and Administration Instructions for Subcutaneous Injection

- OMVOH is intended for use under the guidance and supervision of a healthcare professional. Patients may self-inject OMVOH after training in subcutaneous injection technique. Provide proper training to patients and/or caregivers on the subcutaneous injection technique of OMVOH according to the “Instructions for Use”, included with the packaged product.
- Before injection, remove OMVOH prefilled pens or OMVOH prefilled syringes from the refrigerator, and leave at room temperature for 45 minutes.
- Do not shake the prefilled pens or prefilled syringes.
- Parenteral drug products should be inspected visually for particulate matter and discoloration prior to administration, whenever solution and container permit. The solution should be a clear to opalescent, colorless to slightly yellow to slightly brown solution, and free of visible particles. Do not use OMVOH if it is cloudy, discolored, or there are visible particles.
- Sites for injection include the abdomen, thigh, and back of the upper arm. Instruct patients to inject in a different location (such as upper arms, thighs or any quadrant of abdomen) than the previous injection. Administration of OMVOH in the back of upper arm may only be performed by another person.
- Do not inject into areas where the skin is tender, bruised, erythematous, or indurated.
- OMVOH does not contain preservatives; therefore, discard any unused product. Do not reuse.
- If a dose is missed, administer the dose as soon as possible. Thereafter, resume dosing every 4 weeks.

3 DOSAGE FORMS AND STRENGTHS

OMVOH is a clear to opalescent, colorless to slightly yellow to slightly brown solution available as:

- Intravenous Infusion:
  Injection: 300 mg/15 mL (20 mg/mL) solution in a single-dose vial
- Subcutaneous Use:
  Injection: 100 mg/mL solution in a single-dose prefilled pen
  Injection: 100 mg/mL solution in a single-dose prefilled syringe
  Injection: 200 mg/2 mL solution in a single-dose prefilled pen
  Injection: 200 mg/2 mL (100 mg/mL) solution in a single-dose prefilled syringe

4 CONTRAINDICATIONS

OMVOH is contraindicated in patients with a history of serious hypersensitivity reaction to mirikizumab-mrkz or any of the excipients [see Warnings and Precautions (5.1)].

5 WARNINGS AND PRECAUTIONS

5.1 Hypersensitivity Reactions

Serious hypersensitivity reactions, including anaphylaxis during intravenous infusion, have been reported with OMVOH administration. Infusion-related hypersensitivity reactions, including mucocutaneous erythema and pruritus, were reported during induction [see Adverse Reactions (6.1)]. If a severe hypersensitivity reaction occurs, discontinue OMVOH immediately and initiate appropriate treatment.

5.2 Infections

OMVOH may increase the risk of infection [see Adverse Reactions (6.1)].

Do not initiate treatment with OMVOH in patients with a clinically important active infection until the infection resolves or is adequately treated.

In patients with a chronic infection or a history of recurrent infection, consider the risks and benefits prior to prescribing OMVOH. Instruct patients to seek medical advice if signs or symptoms of clinically important acute or chronic infection occur. If a serious infection develops or an infection is not responding to standard therapy, monitor the patient closely and do not administer OMVOH until the infection resolves.

5.3 Tuberculosis

Evaluate patients for tuberculosis (TB) infection prior to initiating treatment with OMVOH.

Do not administer OMVOH to patients with active TB infection. Initiate treatment of latent TB prior to administering OMVOH. Consider anti-TB therapy prior to initiation of OMVOH in patients with a past history of latent or active TB in whom an adequate course of treatment cannot be confirmed. Monitor patients for signs and symptoms of active TB during and after OMVOH treatment.

In clinical trials, subjects were excluded if they had evidence of active TB, a past history of active TB, or were diagnosed with latent TB at screening.

5.4 Hepatotoxicity

A case of drug-induced liver injury (alanine aminotransferase [ALT] 18x the upper limit of normal (ULN), aspartate aminotransferase [AST] 10x ULN, and total bilirubin 2.4x ULN) in conjunction with pruritus was reported in a clinical trial subject following a longer than recommended induction regimen. OMVOH was discontinued. Liver test abnormalities eventually returned to baseline.

Evaluate liver enzymes and bilirubin at baseline and for at least 24 weeks of treatment. Monitor thereafter according to routine patient management.

Consider other treatment options in patients with evidence of liver cirrhosis. Prompt investigation of the cause of liver enzyme elevation is recommended to identify potential cases of drug-induced liver injury. Interrupt treatment if drug-induced liver injury is suspected, until this diagnosis is excluded. Instruct patients to seek immediate medical attention if they experience symptoms suggestive of hepatic dysfunction.

5.5 Immunizations

Avoid use of live vaccines in patients treated with OMVOH. Medications that interact with the immune system may increase the risk of infection following administration of live vaccines. Prior to initiating therapy with OMVOH, complete all age-appropriate vaccinations according to current immunization guidelines. No data are available on the response to live or non-live vaccines in patients treated with OMVOH.

6 ADVERSE REACTIONS

The following topics are also discussed in detail in the Warnings and Precautions section:

- Hypersensitivity Reactions [see Warnings and Precautions (5.1)]
- Infections [see Warnings and Precautions (5.2)]
- Tuberculosis [see Warnings and Precautions (5.3)]
- Hepatotoxicity [see Warnings and Precautions (5.4)]

6.1 Clinical Trials Experience

Because clinical trials are conducted under widely varying conditions, adverse reaction rates observed in the clinical trials of a drug cannot be directly compared to rates in the clinical trials of another drug and may not reflect the rates observed in practice.

Ulcerative Colitis

OMVOH was studied up to 12 weeks in subjects with moderately to severely active ulcerative colitis in a randomized, double-blind, placebo-controlled induction study (UC-1). In subjects who responded to induction therapy in UC-1, long term safety up to 52 weeks was evaluated in a randomized, double-blind, placebo-controlled maintenance study (UC-2) and a long-term extension study [see Clinical Studies (14.1)].

In the induction study (UC-1), 1279 subjects were enrolled of whom 958 received OMVOH 300 mg administered as an intravenous infusion at Weeks 0, 4, and 8. In the maintenance study (UC-2), 581 subjects were enrolled of whom 389 received OMVOH 200 mg administered as a subcutaneous injection every 4 weeks.

Table 2 summarizes the adverse reactions reported in at least 2% of subjects and at a higher frequency than placebo during UC-1.

Table 2: Adverse Reactionsa in Subjects with Ulcerative Colitis through Week 12 in a Placebo-Controlled Induction Study (UC-1)
Adverse Reactions | OMVOH 300 mg Intravenous Infusionb N=958 n (%) | Placebo N=321 n (%)
Upper respiratory tract infectionsc | 72 (8%) | 20 (6%)
Arthralgia | 20 (2%) | 4 (1%)
a Reported in at least 2% of subjects and at a higher frequency than placebo.
b OMVOH 300 mg as an intravenous infusion at Weeks 0, 4, and 8.
c Upper respiratory tract infections includes related terms (e.g., COVID-19, nasopharyngitis, pharyngitis, rhinitis, sinusitis, and upper respiratory tract infection).

In the induction study (UC-1), infusion-related hypersensitivity reactions were reported by 4 (0.4%) subjects treated with OMVOH and 1 (0.3%) subject treated with placebo.

Table 3 summarizes the adverse reactions reported in at least 2% of subjects and at a higher frequency than placebo during the 40-week controlled period of UC-2.

Table 3: Adverse Reactionsa in Subjects with Ulcerative Colitis through Week 40 In a Placebo-Controlled Maintenance Study (UC-2)
Adverse Reactions | OMVOH 200 mg Subcutaneous Injectionb N=389 n (%) | Placebo N=192 n (%)
Upper respiratory tract infectionsc | 53 (14%) | 23 (12%)
Injection site reactionsd | 34 (9%) | 8 (4%)
Arthralgia | 26 (7%) | 8 (4%)
Rashe | 16 (4%) | 2 (1%)
Headache | 16 (4%) | 2 (1%)
Herpes viral infectionf | 9 (2%) | 1 (1%)
a Reported in at least 2% of subjects and at a higher frequency than placebo
b OMVOH 200 mg as a subcutaneous injection at Week 12 and every 4 weeks thereafter for up to an additional 40 weeks.
c Upper respiratory tract infections includes related terms (e.g., COVID-19, nasopharyngitis, pharyngitis, rhinitis, sinusitis, and upper respiratory tract infection).
d Injection site reactions includes related terms (e.g., erythema, hypersensitivity, pain, reaction, and urticaria at the injection site).
e Rash is composed of several similar terms.
f Herpes viral infection includes related terms (e.g., herpes zoster, herpes simplex, and oral herpes).

Infections

In UC-1 through Week 12, infections were reported by 145 (15%) subjects treated with OMVOH 300 mg and 45 (14%) subjects treated with placebo. Serious infections were reported by less than 1% in both groups. Serious infections in the OMVOH group included intestinal sepsis, listeria sepsis, and pneumonia.

In the maintenance study (UC-2) through Week 40 (a total of 52 weeks of treatment), infections were reported by 93 (24%) subjects treated with OMVOH 200 mg and 44 (23%) subjects treated with placebo. A case of COVID-19 pneumonia was reported as a serious infection in the OMVOH group.

Hepatic Enzyme Elevations

In UC-1 through Week 12, alanine aminotransferase (ALT) ≥5X ULN was reported by 1 (0.1%) subject treated with OMVOH 300 mg and 1 (0.3%) subject treated with placebo. Aspartate aminotransferase (AST) ≥5X ULN was reported by 2 (0.2%) subjects treated with OMVOH 300 mg and no subject treated with placebo. These elevations have been noted with and without concomitant elevations in total bilirubin.

In UC-2 through Week 40 (a total of 52 weeks of treatment), 3 (0.8%) subjects treated with OMVOH 200 mg reported ALT ≥5X ULN and 3 (0.8%) subjects reported AST ≥5X ULN; with or without concomitant elevations in total bilirubin. No subjects treated with placebo experienced similar elevations [see Warnings and Precautions (5.4)].

Crohn's Disease

OMVOH was studied up to 52 weeks in subjects with moderately to severely active Crohn's disease in a randomized, double-blind, placebo-controlled study (CD-1). The safety population consisted of 630 subjects who received OMVOH 900 mg administered as an intravenous infusion during induction at Weeks 0, 4, and 8 followed by OMVOH 300 mg administered as a subcutaneous injection every 4 weeks and 211 subjects who received placebo [see Clinical Trials (14.2)]. Eighty-five of the 211 placebo subjects in the safety population who did not achieve clinical response by patient-reported outcome at Week 12 were switched to blinded induction and maintenance treatment with OMVOH. Observed data from these 85 subjects are included in the placebo cohort up to Week 12 and in the OMVOH cohort after Week 12. In CD-1, OMVOH and placebo-treated subjects had different lengths of exposure, therefore, exposure adjusted incidence rates (EAIRs) are also displayed in Table 4 to compare adverse reactions.

Common Adverse Reactions

Table 4 summarizes the frequencies and EAIRs per 100 person-years (PY) for adverse reactions reported in at least 5% of subjects treated with OMVOH and at a higher frequency than placebo during CD-1.

Table 4: Adverse Reactionsa in Subjects with Crohn's Disease through Week 52 In a Placebo-Controlled Study (CD-1)
Adverse Reactions | OMVOHb N=715, PY=655 n (%) [EAIRc] | Placebo N=211, PY=120 n (%) [EAIRc]
Upper respiratory tract infectionsd | 199 (28) [37] | 47 (22) [47]
Injection site reactionse | 69 (10) [11] | 8 (4) [7]
Headachef | 45 (6) [7] | 9 (4) [8]
Arthralgia | 44 (6) [7] | 11 (5) [10]
Elevated liver testsg | 36 (5) [6] | 8 (4) [7]
Abbreviations: EAIR, exposure-adjusted incidence rate; PY, person-years
a Reported in at least 5% of subjects and at a higher frequency than placebo
b Following OMVOH 900 mg as an intravenous infusion at Week 0, Week 4, and Week 8, subjects received OMVOH 300 mg as a subcutaneous injection at Week 12 and every 4 weeks thereafter for up to an additional 40 weeks. In addition, eighty-five placebo subjects who did not achieve clinical response by patient-reported outcome at Week 12 were switched to blinded induction and maintenance treatment with OMVOH. The observed data after Week 12 from these eighty-five subjects were included in the OMVOH cohort.
c EAIRs are per 100 PY. The EAIR per 100 PY can be interpreted as an estimated number of first occurrences of the adverse reaction of interest if 100 subjects were treated for one year.
d Upper respiratory tract infections includes related terms (e.g., COVID-19, nasopharyngitis, pharyngitis, rhinitis, sinusitis, and upper respiratory tract infection).
e Injection site reactions includes related terms (e.g., erythema, hematoma, induration, pain, pruritus, and reaction at the injection site).
f Headache includes related terms (i.e., headache and migraine).
g Elevated liver tests include related terms (e.g., ALT increased, AST increased, alkaline phosphatase increased, bilirubin increased, and GGT increased)

Hepatic Enzyme Elevations

Of the subjects with reported adverse reactions of elevated liver tests (see Table 4), 3 subjects treated with OMVOH reported ALT ≥5X ULN and 2 subjects reported AST ≥5X ULN. Neither subject had a concomitant elevation in total bilirubin. No subjects treated with placebo experienced similar elevations.

Less Common Adverse Reactions (<5%)

In CD-1 through Week 52, urticaria was reported by 13 (2%, 2 per 100 PY) subjects treated with OMVOH and no subjects treated with placebo.

Infections

In CD-1 through Week 52, infections were reported by 282 (39%, 58 per 100 PY) subjects treated with OMVOH and 73 (35%, 81 per 100 PY) subjects treated with placebo. Serious infections in the OMVOH group included abscess (including abdominal abscess, anal abscess, gluteal abscess, and perineal abscess), cellulitis, pneumonia, and sepsis.

7 DRUG INTERACTIONS

7.1 CYP450 Substrates

Increased concentrations of cytokines (e.g., IL-1, IL-6, IL-10, TNFα, IFN) during chronic inflammation associated with certain diseases including Crohn's disease may suppress the formation of CYP450 enzymes. Therapeutic proteins, including mirikizumab-mrkz, that decrease the concentrations of these pro-inflammatory cytokines may increase the formation of CYP450 enzymes resulting in decreased CYP450 substrate exposure. Upon initiation or discontinuation of OMVOH in patients treated with concomitant CYP450 substrates, monitor drug concentrations or other therapeutic parameters, and adjust the dosage of the CYP450 substrate as needed. See the prescribing information of specific CYP450 substrates.

8 USE IN SPECIFIC POPULATIONS

8.1 Pregnancy

Pregnancy Exposure Registry

There will be a pregnancy exposure registry that monitors pregnancy outcomes in women exposed to OMVOH during pregnancy. Pregnant women exposed to OMVOH and healthcare providers are encouraged to call Eli Lilly and Company at 1-800-Lilly-Rx (1-800-545-5979).

Risk Summary

Available data from case reports of mirikizumab-mrkz use in pregnant women are insufficient to evaluate for a drug-associated risk of major birth defects, miscarriage, or other adverse maternal or fetal outcomes. Although there are no data on mirikizumab-mrkz, monoclonal antibodies can be actively transported across the placenta, and mirikizumab-mrkz may cause immunosuppression in the in utero-exposed infant. An enhanced pre- and post-natal development study conducted in pregnant monkeys at a dose 20 times the maximum recommended human dose (MRHD) revealed no adverse developmental effects to the developing fetus, or harm to infant monkeys from birth through 6 months of age. There are risks of adverse pregnancy outcomes associated with increased disease activity in women with inflammatory bowel disease (see Clinical Considerations).

The background risk of major birth defects and miscarriage for the indicated population is unknown. All pregnancies have a background risk of birth defects, loss, or other adverse outcomes. In the U.S. general population, the estimated background risk of major birth defects and miscarriage in clinically recognized pregnancies is 2% to 4% and 15% to 20%, respectively.

Clinical Considerations

Disease-Associated Maternal and Embryo/Fetal Risk

Published data suggest that the risk of adverse pregnancy outcomes in women with inflammatory bowel disease (IBD) is associated with increased disease activity. Adverse pregnancy outcomes include preterm delivery (before 37 weeks gestation), low birth weight (less than 2500 g) infants, and small for gestational age at birth.

Fetal/Neonatal Adverse Reactions

Transport of endogenous IgG antibodies across the placenta increases as pregnancy progresses, and peaks during the third trimester. It is unclear whether mirikizumab-mrkz may interfere with an infant's immune response to infections. Therefore, monitoring for the development of serious infection during the first 2 months of life in infants exposed in utero is recommended.

Data

Animal Data

An enhanced pre- and postnatal development study was conducted in cynomolgus monkeys administered mirikizumab-mrkz by intravenous injection during organogenesis to parturition at a dose of 300 mg/kg twice weekly (20 times the MRHD based on exposure comparisons). Mirikizumab-mrkz crossed the placenta in monkeys. No maternal toxicity was noted in this study. No mirikizumab-mrkz-related effects on morphological, functional or immunological development were observed in infant monkeys from birth through 6 months of age. However, incidences of embryo/fetal loss were higher in the treated groups compared to control (6.7% [1 of 15] in controls vs 26.7% [4 of 15] at 300 mg/kg (20 times the MRHD, based on exposure comparisons) but were within the range of historical control data. Following delivery, most adult female cynomolgus monkeys and all infants from the mirikizumab-mrkz-treated group had measurable serum concentrations up to 28 days postpartum. In the infant monkeys, mean serum concentrations were approximately 4.8 times the respective mean maternal concentrations.

8.2 Lactation

Risk Summary

There are no data on the presence of mirikizumab-mrkz in human milk, the effects on the breastfed infant, or the effects on milk production. Endogenous maternal IgG and monoclonal antibodies are transferred in human milk. The effects of local gastrointestinal exposure and limited systemic exposure in the breastfed infant to mirikizumab-mrkz are unknown. The developmental and health benefits of breastfeeding should be considered along with the mother's clinical need for OMVOH and any potential adverse effects on the breastfed infant from OMVOH or from the underlying maternal condition.

8.4 Pediatric Use

The safety and effectiveness of OMVOH have not been established in pediatric patients.

8.5 Geriatric Use

Of the 795 OMVOH-treated subjects in the two ulcerative colitis clinical studies, 64 subjects (8%) were 65 years of age and older, while 10 subjects (1%) were 75 years of age and older. Of the 715 OMVOH-treated subjects in the Crohn's disease clinical study, 22 subjects (3%) were 65 years of age and older, while 6 subjects (1%) were 75 years of age and older). These clinical studies did not include sufficient numbers of subjects aged 65 and over to determine whether they respond differently from younger adult subjects. Other reported clinical experience has not identified differences in responses between the elderly and younger subjects. No clinically meaningful differences in the pharmacokinetics of mirikizumab-mrkz were observed in subjects 65 years of age and older compared to younger adult subjects [see Clinical Pharmacology (12.3)].

11 DESCRIPTION

Mirikizumab-mrkz is a humanized immunoglobulin G4 (IgG4) variant monoclonal antibody that is directed against the p19 subunit of IL-23 and does not bind IL-12. Mirikizumab-mrkz is produced in Chinese Hamster Ovary (CHO) cells by recombinant DNA technology and it is composed of two identical light chain polypeptides and two identical heavy chain polypeptides with an overall molecular weight of approximately 147 kDa.

OMVOH for intravenous infusion for ulcerative colitis and Crohn's disease

OMVOH (mirikizumab-mrkz) injection is a sterile, preservative-free, clear to opalescent, colorless to slightly yellow to slightly brown solution in a single-dose vial for intravenous infusion after dilution.

OMVOH injection 300 mg /15 mL vial is available in 2 formulations:

- Each mL contains 20 mg of mirikizumab-mrkz, anhydrous citric acid (0.4 mg), polysorbate 80 (0.5 mg), sodium chloride (8.8 mg), sodium citrate (2.1 mg), and Water for Injection. The OMVOH solution has a pH range of 5.0 to 6.0.
- Each mL contains 20 mg of mirikizumab-mrkz, anhydrous citric acid (0.1 mg), histidine (0.1 mg), L-histidine hydrochloride monohydrate (0.9 mg), mannitol (33 mg), polysorbate 80 (0.5 mg), sodium chloride (2.9 mg), sodium citrate (0.2 mg), and Water for Injection. The OMVOH solution has a pH range of 5.0 to 5.8.

OMVOH (mirikizumab-mrkz) injection 100 mg/mL prefilled pen or prefilled syringe for subcutaneous use for ulcerative colitis and Crohn's disease

OMVOH (mirikizumab-mrkz) injection is a sterile, preservative free, clear to opalescent, colorless to slightly yellow to slightly brown solution for subcutaneous use available as 100 mg of mirikizumab-mrkz in a 1 mL single-dose prefilled pen or single-dose prefilled syringe. The prefilled pen and prefilled syringe contain a 1 mL glass syringe with a fixed 27-gauge ½ inch needle. The OMVOH 100 mg prefilled pen and prefilled syringe are manufactured to deliver 100 mg of mirikizumab-mrkz.

Each mL is composed of 100 mg mirikizumab-mrkz, histidine (0.1 mg), L-histidine hydrochloride monohydrate (0.9 mg), mannitol (33 mg), polysorbate 80 (0.3 mg), sodium chloride (2.9 mg), and Water for Injection. The OMVOH solution has a pH range of 5.0 to 5.8.

OMVOH (mirikizumab-mrkz) injection 200 mg/2 mL prefilled pen or 200 mg/2 mL (100 mg/mL) prefilled syringe for subcutaneous use for ulcerative colitis and Crohn's disease

OMVOH (mirikizumab-mrkz) injection is a sterile, preservative free, clear to opalescent, colorless to slightly yellow to slightly brown solution for subcutaneous use. The 2 mL prefilled pen and prefilled syringe each contain a 2 mL glass syringe with a fixed 27-gauge 8 mm needle. The OMVOH 200 mg prefilled pen and prefilled syringe are manufactured to deliver 200 mg of mirikizumab-mrkz.

Each mL is composed of 100 mg mirikizumab-mrkz, histidine (0.1 mg), L-histidine hydrochloride monohydrate (0.9 mg), mannitol (33 mg), polysorbate 80 (0.3 mg), sodium chloride (2.9 mg), and Water for Injection. The OMVOH solution has a pH range of 5.0 to 5.8.

12 CLINICAL PHARMACOLOGY

12.1 Mechanism of Action

Mirikizumab-mrkz is a humanized IgG4 monoclonal antibody that selectively binds to the p19 subunit of human IL-23 cytokine and inhibits its interaction with the IL-23 receptor.

IL-23 is involved in mucosal inflammation and affects the differentiation, expansion, and survival of T cell subsets, and innate immune cell subsets, which represent sources of pro-inflammatory cytokines. Research in animal models has shown that pharmacologic inhibition of IL-23p19 can ameliorate intestinal inflammation.

Mirikizumab-mrkz inhibits the release of pro-inflammatory cytokines and chemokines.

12.2 Pharmacodynamics

In both study UC-1 (induction) and study UC-2 (maintenance), a positive relationship was observed between Mirikizumab-mrkz average concentration and rates of clinical remission and clinical response [see Clinical Studies (14.1)].

Mirikizumab exposure response relationships have not been fully characterized in subjects with Crohn's disease.

12.3 Pharmacokinetics

Mirikizumab-mrkz exhibited linear pharmacokinetics with dose-proportional increase in exposure over a dose range of 60 to 2400 mg given as an intravenous injection or over a dose range of 200 to 400 mg given as a subcutaneous injection, in healthy volunteers. There was no apparent accumulation of mirikizumab-mrkz concentrations in serum over time when administered as a subcutaneous injection every 4 weeks to subjects with ulcerative colitis or Crohn's disease. The estimated exposure parameters of mirikizumab-mrkz at steady state are summarized in Tables 5 for ulcerative colitis and 6 for Crohn's disease.

Table 5: Mirikizumab-mrkz Estimated Systemic Exposure at Steady State in Subjects with Ulcerative Colitis
 | OMVOH 300 mg Intravenous Infusiona Geometric mean (CV%) | OMVOH 200 mg Subcutaneous Injectionb Geometric mean (CV%)
Cmax, ss (μg/mL)c | 99.7 (22.7%) | 10.1 (52.1%)
AUCtau, ss (μg*day/mL)c | 538 (34.4%) | 160 (57.6%)
Ctrough, ss (μg/mL)c | 2.75 (101%) | 1.70 (83.3%)
a OMVOH 300 mg as an intravenous infusion over at least 30 minutes at Weeks 0, 4, and 8.
b OMVOH 200 mg as 2 subcutaneous injections (100 mg/mL each) at Week 12 and every 4 weeks thereafter for up to an additional 40 weeks.
c AUCtau, ss = area under the concentration-versus-time curve over one dosing interval at steady state; Cmax, ss = maximum concentration at steady state; Ctrough, ss = concentration at the end of the dosing interval at steady state; CV = geometric coefficient of variation.

Table 6: Mirikizumab-mrkz Estimated Systemic Exposure at Steady State in Subjects with Crohn's Disease
 | OMVOH 900 mg Intravenous Infusiona Geometric mean (CV%) | OMVOH 300 mg Subcutaneous Injectionb Geometric mean (CV%)
Cmax, ss (μg/mL)c | 332 (21%) | 13.6 (48%)
AUCtau, ss (μg*day/mL)c | 1820 (38%) | 220 (56%)
Ctrough, ss (μg/mL)c | 10.4 (108%) | 2.52 (88%)
a OMVOH 900 mg as an intravenous infusion over at least 90 minutes at Weeks 0, 4, and 8.
b OMVOH 300 mg as 2 subcutaneous injections (100 mg/mL and 200 mg/2 mL) at Week 12 and every 4 weeks thereafter up to Week 52.
c AUCtau, ss = area under the concentration-versus-time curve over one dosing interval at steady state; Cmax, ss = maximum concentration at steady state; Ctrough, ss = concentration at the end of the dosing interval at steady state; CV = geometric coefficient of variation.

Absorption

Following subcutaneous dosing of OMVOH for ulcerative colitis median (range) Tmax was 5 (3.08 to 6.75) days post dose and geometric mean (CV%) absolute bioavailability was 44% (34%).

Following subcutaneous dosing of OMVOH for Crohn's disease, median (range) Tmax was 5 (3 to 6.83) days post dose and geometric mean (CV%) absolute bioavailability was 36.3% (31%).

Injection site location (abdomen, upper arm, or thigh) did not significantly influence bioavailability of mirikizumab-mrkz following subcutaneous injection.

Distribution

In subjects with ulcerative colitis, the geometric mean (CV%) total volume of distribution was 4.83 L (21%).

In subjects with Crohn's disease, the geometric mean (CV%) total volume of distribution was 4.4 L (14%).

Metabolism/Elimination

Mirikizumab-mrkz is a humanized IgG4 monoclonal antibody and is expected to be degraded into small peptides and amino acids via catabolic pathways in the same manner as endogenous IgG.

In subjects with ulcerative colitis, the geometric mean (CV%) clearance was 0.0229 L/hours (34%) and the geometric mean (CV%) elimination half-life was 9.3 days (40%). Clearance is independent of dose.

In subjects with Crohn's disease, the geometric mean (CV%) clearance was 0.0202 L/hours (38%) and the geometric mean (CV%) elimination half-life was 9.3 days (26%). Clearance is independent of dose.

Specific Populations

There were no clinically significant differences in the pharmacokinetics of mirikizumab-mrkz based on age (18 to 79 years), sex, race (White or Asian), or mild and moderate renal impairment (i.e., estimated creatinine clearance by Cockcroft-Gault equation: 30 to 89 mL/min).

Body Weight

Following intravenous administration of 300 mg, the recommended induction dose, in subjects with ulcerative colitis weighing 90 kg or greater, the estimated geometric mean mirikizumab-mrkz average concentration (Cavg) was 20% lower compared with subjects weighing less than 90 kg. Following subcutaneous administration of 200 mg, the recommended maintenance dose, in subjects with ulcerative colitis weighing 90 kg or greater, the estimated geometric mean Cavg was 38% lower compared with subjects weighing less than 90 kg. In Study UC-2 (maintenance), the rate of clinical remission and clinical response did not differ significantly between subjects weighing 90 kg or greater and subjects weighing less than 90 kg.

Following intravenous administration of 900 mg, the recommended induction dose, in subjects with Crohn's disease weighing 90 kg or greater, the estimated geometric mean mirikizumab-mrkz Cavg was 13% lower compared with subjects weighing less than 90 kg. Following subcutaneous administration of 300 mg, the recommended maintenance dose, in subjects with Crohn's disease weighing 90 kg or greater, the estimated geometric mean Cavg was 34% lower compared with subjects weighing less than 90 kg. The rate of clinical remission and clinical response in Crohn's disease did not differ significantly between subjects weighing 90 kg or greater and subjects weighing less than 90 kg.

Drug Interaction Studies

Population pharmacokinetic analyses indicated that the clearance of OMVOH was not impacted by concomitant administration of aminosalicylates, corticosteroids, or oral immunomodulators (6-MP, AZA, MTX, tioguanine) in subjects with ulcerative colitis or Crohn's disease.

No drug-drug interaction studies were conducted in subjects with ulcerative colitis or Crohn's disease at the recommended dosage. Based on a clinical drug-drug interaction study conducted in subjects with another condition, multiple subcutaneous doses of 250 mg every 4 weeks of mirikizumab-mrkz did not result in changes in the exposure of midazolam (CYP3A substrate), warfarin (CYP2C9 substrate), dextromethorphan (CYP2D6 substrate), omeprazole (CYP2C19 substrate), or caffeine (CYP1A2 substrate).

12.6 Immunogenicity

The observed incidence of anti-drug antibodies is highly dependent on the sensitivity and specificity of the assay. Differences in assay methods preclude meaningful comparisons of the incidence of anti-drug antibodies in the studies described below with the incidence of anti-drug antibodies in other studies, including those of mirikizumab-mrkz or of other mirikizumab products.

During the 52-week treatment period in studies UC-1 and UC-2, 23% (88/378) of OMVOH-treated subjects at the recommended dosage and evaluable for assessment, developed anti-mirikizumab-mrkz antibodies (referred to as anti-drug antibodies (ADA)). Of those who developed ADA, 33/88 (38%) developed titers ≥1:160. Of these 33 OMVOH-treated subjects, 10 had reduced serum trough concentrations of mirikizumab-mrkz compared to subjects who did not develop anti-mirikizumab-mrkz antibodies, and 5 of these 10 subjects did not achieve clinical response at Week 52. There is insufficient data to assess whether the observed ADA-associated pharmacokinetic changes reduced effectiveness. There is no identified clinically significant effect of ADA on the safety of OMVOH over the treatment duration of 52-weeks.

During the 52-week treatment period in study CD-1, 13% (79/622) of OMVOH-treated subjects at the recommended dosage and evaluable for assessment developed ADA. There is no identified clinically significant effect of ADA on the pharmacokinetics, effectiveness, or safety of OMVOH over the treatment duration of 52-weeks.

13 NONCLINICAL TOXICOLOGY

13.1 Carcinogenesis, Mutagenesis, Impairment of Fertility

Animal studies have not been conducted to evaluate the carcinogenic or mutagenic potential of mirikizumab-mrkz.

No organ weight or histopathology effects were observed in the male or female reproductive tract in sexually mature cynomolgus monkeys that received subcutaneous mirikizumab-mrkz once weekly for 26 weeks, at a dose of 100 mg/kg (at least 2 times the MRHD of mirikizumab-mrkz, based on exposure comparisons).

14 CLINICAL STUDIES

14.1 Ulcerative Colitis

The safety and efficacy of OMVOH was evaluated in two randomized, double-blind, placebo-controlled clinical studies, one induction study [UC-1 (NCT03518086)] and one maintenance study [UC-2 (NCT03524092)], in adult subjects with moderately to severely active ulcerative colitis who had inadequate response, loss of response, or failed to tolerate any of the following: corticosteroids, 6-mercaptopurine, azathioprine, biologic therapy (TNF blocker, vedolizumab), or tofacitinib. The 12-week intravenous induction study (UC-1) was followed by the 40-week subcutaneous randomized withdrawal maintenance study (UC-2).

Study UC-1

In UC-1, efficacy was evaluated in 1062 subjects who were randomized 3:1 at Week 0 to receive 300 mg OMVOH or placebo by intravenous infusion at Week 0, Week 4, and Week 8. Subjects had a mean age of 43 years (range 18 to 79 years); 40% were female; and 71% identified as White, 25% as Asian, 1% as American Indian or Alaska Native, 1% as Black or African American, and <2% as another racial group or did not report their racial group. Subjects were permitted to use stable doses of aminosalicylates, immunomodulators (6-mercaptopurine, azathioprine, methotrexate), and oral corticosteroids (prednisone ≤20 mg/day or equivalent, extended-release budesonide 9 mg/day, beclomethasone dipropionate 5 mg/day). At baseline, 41% of subjects were receiving oral corticosteroids, 24% were receiving immunomodulators, and 75% were receiving aminosalicylates.

At baseline, 57% were biologic and Janus Kinase inhibitor (JAKi) naive, 41% had failed at least one biologic, 3% had failed a JAKi, and 2% had previously received but had not failed a biologic or JAKi.

Disease activity was assessed based on the modified Mayo score (mMS), which ranges from 0 to 9 and has three subscores that are each scored from 0 (normal) to 3 (most severe): stool frequency, rectal bleeding, and findings on centrally read endoscopy subscore. At baseline, subjects had a mMS of 5 to 9, including a centrally read endoscopy subscore of 2 or 3. An endoscopy subscore of 2 was defined by marked erythema, absent vascular pattern, friability, and erosions; and a subscore of 3 was defined by spontaneous bleeding and ulceration. Subjects had a median mMS of 7, and 58% had severely active disease (mMS of 7 to 9).

The primary endpoint was clinical remission at Week 12. The secondary endpoints were clinical response, endoscopic improvement, and histologic-endoscopic mucosal improvement (see Table 7).

Table 7: Proportion of Subjects with Ulcerative Colitis Meeting Efficacy Endpoints in UC-1 at Week 12
Endpoint | Placebo | OMVOH 300 mg Intravenous Infusiona | Treatment Differenceb (95% CI)
Clinical remissionc
Total Population | N = 267 15% | N = 795 24% | 10%d (5, 15)
Biologic and JAKi naive | N = 155 18% | N = 450 31%
Prior biologic or JAKi failuree | N = 107 8% | N = 331 15%
Clinical responsef
Total Population | N = 267 43% | N = 795 65% | 22%d (15, 28)
Biologic and JAKi naive | N = 155 52% | N = 450 71%
Prior biologic or JAKi failured, e | N = 107 31% | N = 331 56%
Endoscopic improvementg
Total Population | N = 267 21% | N = 795 34% | 14%d (8, 20)
Biologic and JAKi naive | N = 155 28% | N = 450 44%
Prior biologic or JAKi failuree | N = 107 10% | N = 331 22%
Histologic-endoscopic mucosal improvementh
Total Population | N = 267 14% | N = 795 25% | 11%d (6, 16)
Biologic and JAKi naive | N = 155 19% | N = 450 34%
Prior biologic or JAKi failuree | N = 107 7% | N = 331 13%
JAKi = Janus Kinase inhibitor
a OMVOH 300 mg as an intravenous infusion at Week 0, Week 4, and Week 8.
b Adjusted treatment difference based on Cochran-Mantel-Haenszel method adjusted for randomization stratification factors.
c Clinical remission based on mMS is defined as: stool frequency subscore = 0 or 1, rectal bleeding subscore = 0, and centrally read endoscopy subscore = 0 or 1 (excluding friability).
d Tested at an alpha level of 0.00125, with a p-value <0.001.
e Prior biologic or JAKi failure includes loss of response, inadequate response, or intolerance to one or more biologic therapy (TNF blocker or vedolizumab), or tofacitinib.
f Clinical response is defined as a decrease in the mMS of ≥2 points with ≥30% decrease from baseline, and either a decrease of ≥1 point in the rectal bleeding subscore from baseline or a rectal bleeding subscore of 0 or 1.
g Endoscopic improvement is defined as a centrally read endoscopy subscore of 0 or 1 (excluding friability).
h Histologic-endoscopic mucosal improvement is defined as achieving both endoscopic improvement (centrally read endoscopy subscore of 0 or 1, excluding friability) and histologic improvement (neutrophil infiltration in <5% of crypts, no crypt destruction, and no erosions, ulcerations, or granulation tissue based on the Geboes scoring system).

Study UC-1 was not designed to evaluate the relationship of histologic-endoscopic mucosal improvement at Week 12 to disease progression and long-term outcomes.

Rectal Bleeding and Stool Frequency Subscores

Decreases in rectal bleeding and stool frequency subscores were observed as early as Week 3 in subjects treated with OMVOH compared to subjects on placebo.

Study UC-2

The maintenance study (UC-2) evaluated 506 subjects who achieved clinical response at Week 12 in Study UC-1. These subjects were randomized 2:1 to receive 200 mg OMVOH or placebo subcutaneously every 4 weeks for 40 weeks in UC-2, for a total of 52 weeks of treatment. Subjects who were on concomitant ulcerative colitis therapies during UC-1 were required to continue on stable doses of oral aminosalicylates and immunomodulators (6-mercaptopurine, azathioprine, methotrexate). Corticosteroid tapering was required for subjects who were receiving corticosteroids at baseline and achieved clinical response in UC-1.

The primary endpoint was clinical remission at Week 40. The secondary endpoints were endoscopic improvement, maintenance of clinical remission in subjects who achieved clinical remission at Week 12, corticosteroid-free clinical remission, and histologic-endoscopic mucosal improvement (see Table 8).

Table 8: Proportion of Subjects with Ulcerative Colitis Meeting Efficacy Endpoints in UC-2 at Week 40 (a total of 52 weeks of treatment)
Endpoint | Placeboa | OMVOH 200 mg Subcutaneous Injectionb | Treatment Differencec (95% CI)
Clinical remissiond, e
Total Population | N = 169 27% | N = 337 51% | 22%f (14, 31)
Biologic and JAKi naive | N = 109 33% | N = 208 53%
Prior biologic or JAKi failureg | N = 59 15% | N = 121 45%
Endoscopic improvementd, h
Total Population | N = 169 30% | N = 337 58% | 27%f (19, 36)
Biologic and JAKi naive | N = 109 35% | N = 208 62%
Prior biologic or JAKi failureg | N = 59 20% | N = 121 50%
Maintenance of clinical remission in patients who achieved clinical remission at Week 12i
Total Population | N = 62 40% | N = 128 66% | 23%j (8, 38)
Biologic and JAKi naive | N = 48 48% | N = 91 66%
Prior biologic or JAKi failureg | N = 14 14% | N = 34 65%
Corticosteroid-free clinical remissiond, k
Total Population | N = 169 27% | N = 337 50% | 22%f (13, 30)
Biologic and JAKi naive | N = 109 33% | N = 208 52%
Prior biologic or JAKi failureg | N = 59 15% | N = 121 45%
Histologic-endoscopic mucosal improvementd, l
Total Population | N = 169 22% | N = 337 43% | 19%f (11, 27)
Biologic and JAKi naive | N = 109 27% | N = 208 47%
Prior biologic or JAKi failureg | N = 59 14% | N = 121 36%
JAKi = Janus Kinase inhibitor
a The placebo arm includes subjects treated with OMVOH during the induction study (UC-1) and were randomized to receive placebo through Week 40.
b OMVOH 200 mg as a subcutaneous injection at Week 12 and every 4 weeks thereafter for up to an additional 40 weeks.
c Adjusted treatment difference (95% CI) based on Cochran-Mantel-Haenszel method adjusted for randomization stratification factors.
d Among subjects who achieved clinical response at Week 12 in UC-1 with OMVOH induction treatment.
e Clinical remission based on mMS is defined as: stool frequency subscore = 0 or 1, rectal bleeding subscore = 0, and centrally read endoscopy subscore = 0 or 1 (excluding friability).
f p<0.001.
g Prior biologic or JAKi failure includes loss of response, inadequate response, or intolerance to one or more biologic therapy (TNF blocker or vedolizumab), or tofacitinib.
h Endoscopic improvement is defined as a centrally read endoscopy subscore of 0 or 1 (excluding friability).
i Among subjects who achieved clinical remission at Week 12 in UC-1 with OMVOH induction treatment.
j p<0.01.
k Corticosteroid-free clinical remission is defined as clinical remission at Week 40 and no corticosteroid use for ≥12 weeks prior to Week 40 assessment.
l Histologic-endoscopic mucosal improvement is defined as achieving both endoscopic improvement (centrally read endoscopy subscore of 0 or 1, excluding friability) and histologic improvement (no neutrophils in crypts or lamina propria, no crypt destruction, and no erosions, ulcerations, or granulation tissue based on the Geboes scoring system).

Study UC-2 was not designed to evaluate the relationship of histologic-endoscopic mucosal improvement at Week 40 to disease progression and long-term outcomes.

Bowel Urgency

Bowel urgency was assessed during UC-1 and UC-2 with an Urgency Numeric Rating Scale (NRS) of 0 to 10. A greater proportion of subjects with a baseline Urgency NRS weekly average score ≥3 treated with OMVOH compared to placebo reported an Urgency NRS weekly average score of 0 or 1 (39% versus 23%) at Week 40. Urgency NRS weekly average scores of 0 to 1 were also observed in a greater proportion of subjects treated with OMVOH compared to placebo at Week 12.

Endoscopic Assessment

Normalization of the endoscopic appearance of the mucosa (endoscopic remission) was defined as a Mayo endoscopic subscore of 0. At Week 40 in UC-2, endoscopic remission was observed in a greater proportion of subjects treated with OMVOH compared to placebo (22% versus 14%).

14.2 Crohn's Disease

The safety and efficacy of OMVOH was evaluated in a randomized, double-blind, placebo-controlled study [CD-1 (NCT03926130)] in adult subjects with moderately to severely active Crohn's disease who had an inadequate response, loss of response, or intolerance to corticosteroids, immunomodulators (azathioprine, 6-mercaptopurine, and methotrexate), and/or biologics (TNF blockers, integrin receptor antagonists).

In CD-1, the efficacy population consisted of 679 subjects who were randomized 3:1 at Week 0 to receive OMVOH 900 mg by intravenous infusion at Week 0, Week 4, and Week 8 followed by a dosage of 300 mg by subcutaneous injection at Week 12 and then every 4 weeks for 40 weeks, or placebo. Subjects had a mean age of 36 years (range 18 to 74 years); 42% were female; and 71% identified as White, 25% as Asian, <1% as American Indian or Alaska Native, 1% as Black or African American, and 2% as another racial group or did not report their racial group. Subjects were permitted to use stable doses of oral corticosteroids (prednisone ≤30 mg/day or equivalent, extended-release budesonide 9 mg/day), immunomodulators (6-mercatopurine, azathioprine, or methotrexate) and/or aminosalicylates. At baseline, 31% of subjects were receiving oral corticosteroids, 26% were receiving immunomodulators, and 44% were receiving aminosalicylates.

At baseline, 47% had a loss of response, inadequate response, or intolerance to one or more biologic therapy.

Disease activity at baseline was assessed by the Crohn's Disease Activity Index (CDAI) and the Simple Endoscopic Score for Crohn's disease (SES-CD). Moderately to severely active CD was defined by a CDAI of ≥220 and an SES-CD ≥7 (centrally read) for subjects with ileal-colonic disease or ≥4 for subjects with isolated ileal disease. At baseline, subjects had a median CDAI of 329 and SES-CD of 12.

The coprimary endpoints of clinical remission by CDAI and endoscopic response by SES-CD were assessed at Week 52. Secondary efficacy endpoints included endoscopic response at Week 12 and endoscopic remission and corticosteroid-free clinical remission at Week 52 (see Table 9).

Table 9: Proportion of Subjects with Crohn's Disease Meeting Efficacy Endpoints in CD-1
 | Placeboa | OMVOHb | Treatment Differencec (95% CI)
Coprimary Endpoints
Clinical remissiond at Week 52
Total population | N = 168 36% | N = 511 53% | 17%e (9%, 25%)
Without prior biologic failure | N = 89 45% | N = 268 56%
Prior biologic failuref | N = 79 25% | N = 243 49%
Endoscopic responseg at Week 52
Total population | N = 168 23% | N = 511 46% | 23%e (15%, 30%)
Without prior biologic failure | N = 89 27% | N = 268 49%
Prior biologic failuref | N = 79 18% | N = 243 43%
Additional Endpoints
Endoscopic responseg at Week 12
Total population | N = 168 11% | N = 511 32% | 22%e (16%, 28%)
Without prior biologic failure | N = 89 12% | N = 268 37%
Prior biologic failuref | N = 79 9% | N = 243 28%
Corticosteroid-free clinical remissioni at Week 52
Total population | N = 168 35% | N = 511 50% | 16% e (7%, 24%)
Without prior biologic failure | N = 89 43% | N = 268 54%
Prior biologic failuref | N = 79 25% | N = 243 46%
Endoscopic remissionh at Week 52
Total population | N = 168 8% | N = 511 19% | 11% e (6%, 16%)
Without prior biologic failure | N = 89 10% | N = 268 22%
Prior biologic failuref | N = 79 5% | N = 243 16%
CI = confidence interval
a The placebo group includes all 168 subjects randomized to placebo at baseline. Of those, 67 (40%) subjects who did not achieve clinical response by patient-reported outcome at Week 12 were switched to treatment with OMVOH and their efficacy data are included here with the remaining subjects randomized to placebo who did not receive OMVOH.
b Following OMVOH 900 mg as an intravenous infusion at Week 0, Week 4, and Week 8, subjects received OMVOH 300 mg as a subcutaneous injection at Week 12 and every 4 weeks thereafter for up to an additional 40 weeks.
c Adjusted treatment difference was based on Cochran-Mantel-Haenszel method adjusted for randomization stratification factors.
d Clinical remission is defined as CDAI <150.
e p-value <0.001.
f Prior biologic failure includes loss of response, inadequate response, or intolerance to one or more biologic therapy (TNF blockers, and integrin receptor antagonists).
g Endoscopic response is defined as >50% reduction from baseline in SES-CD total score, based on central reading.
h Endoscopic remission is defined as SES-CD total score ≤4 and at least a 2-point reduction from baseline, with no segment subscore >1, based on central reading.
i Corticosteroid-free clinical remission is defined as subjects who were corticosteroid-free from Week 40 to Week 52, and had a CDAI <150 at Week 52.

Stool Frequency and Abdominal Pain

In CD-1, reductions in abdominal pain were observed as early as Week 6 and in stool frequency as early as Week 12 in subjects treated with OMVOH compared to placebo.

Fatigue

In CD-1, subjects treated with OMVOH experienced a clinically meaningful improvement in fatigue, assessed by the change from baseline in the Functional Assessment of Chronic Illness Therapy Fatigue Scale (FACIT-Fatigue), at Week 12, compared to placebo-treated subjects. The effect of OMVOH to improve fatigue after 12 weeks has not been established.

Other Assessments at Week 12

In CD-1, a greater proportion of subjects treated with OMVOH compared to placebo achieved clinical remission (34% versus 23%) and endoscopic remission (10% versus 4%) at Week 12.

16 HOW SUPPLIED/STORAGE AND HANDLING

OMVOH (mirikizumab-mrkz) injection is a sterile, preservative-free, clear to opalescent, colorless to slightly yellow to slightly brown solution for intravenous infusion or subcutaneous injection.

OMVOH is supplied in indication specific packaging as:

Table 10: Packaging Information for OMVOH
Presentation | Indication | Package Size | NDC Code
Single-dose Vial
300 mg/15 mL (20 mg/mL) | Ulcerative colitis and Crohn's disease | Carton of 1 | 0002-7575-01
Single-dose Prefilled Pen
100 mg/mL + 100 mg/mL | Ulcerative colitis | Carton of 2 | 0002-8011-27
200 mg/2 mL | Ulcerative colitis | Carton of 1 | 0002-3116-11
200 mg/2 mL + 100 mg/mL | Crohn's disease | Carton of 2 (1 of each) | 0002-7717-11
Single-dose Prefilled Syringe
100 mg/mL + 100 mg/mL | Ulcerative colitis | Carton of 2 | 0002-8870-27
200 mg/2 mL (100 mg/mL) | Ulcerative colitis | Carton of 1 | 0002-1442-11
200 mg/2 mL (100 mg/mL) + 100 mg/mL | Crohn's disease | Carton of 2 (1 of each) | 0002-7722-11

Note to Pharmacist: The entire carton of 2 prefilled pen or 2 prefilled syringes are to be dispensed as a unit.

Each 100 mg/mL single-dose prefilled pen or prefilled syringe consists of a 1 mL glass syringe with a fixed 27-gauge ½ inch needle.

Each 200 mg/2 mL single-dose prefilled pen or 200 mg/2 mL (100 mg/mL) prefilled syringe consists of a 2 mL glass syringe with a fixed 27-gauge 8 mm needle.

Storage and Handling

- Store refrigerated at 2°C to 8°C (36°F to 46°F).
- Do not freeze. Do not use OMVOH if it has been frozen.
- Do not shake.
- Keep OMVOH in the original carton to protect from light until the time of use.
- OMVOH is sterile and preservative-free. Discard any unused portion.
- If needed, the prefilled pen or prefilled syringe may be stored at room temperature up to 30°C (86°F) for up to 2 weeks in the original carton to protect from light. Once OMVOH has been stored at room temperature, do not return to the refrigerator. If these conditions are exceeded, OMVOH must be discarded.
- The vial, prefilled pen, and prefilled syringe are not made with dry natural rubber latex.

17 PATIENT COUNSELING INFORMATION

Advise the patient and/or caregiver to read the FDA-approved patient labeling (Medication Guide and Instructions for Use).

Hypersensitivity Reactions

Advise patients to discontinue OMVOH and seek immediate medical attention if they experience any symptoms of serious hypersensitivity reactions [see Warnings and Precautions (5.1)].

Infections

Advise patients that OMVOH may lower the ability of their immune system to fight infections and to contact their healthcare provider immediately if they develop any symptoms of infection [see Warnings and Precautions (5.2)].

Tuberculosis

Advise patients to contact their healthcare provider if they experience symptoms suggestive of TB (e.g., unexplained fever, cough, or difficulty breathing) [see Warnings and Precautions (5.3)].

Hepatotoxicity

Inform patients that OMVOH may cause liver injury. Advise patients to seek immediate medical attention if they experience symptoms suggestive of liver dysfunction (e.g., unexplained rash, nausea, vomiting, abdominal pain, fatigue, anorexia, or jaundice and/or dark urine) [see Warnings and Precautions (5.4)].

Immunizations

Advise patients that vaccination with live vaccines is not recommended during OMVOH treatment and immediately prior to or after OMVOH treatment. Medications that interact with the immune system may increase the risk of infection following administration of live vaccines. Instruct patients to inform their healthcare provider that they are taking OMVOH prior to receiving a vaccination [see Warnings and Precautions (5.5)].

Pregnancy

Advise patients who are exposed to OMVOH during pregnancy to contact Eli Lilly and Company [see Use in Specific Populations (8.1)].

Administration

Instruct patients in preparation and administration of OMVOH, including choosing anatomical sites for subcutaneous administration, and proper subcutaneous injection technique. Instruct patients in the technique of prefilled pen or prefilled syringe disposal [see Instructions for Use].

Instruct ulcerative colitis patients or caregivers to administer either:

- Two 100 mg prefilled pens or two 100 mg prefilled syringes to achieve the full 200 mg dose of OMVOH.
- One 200 mg prefilled pen or one 200 mg prefilled syringe to achieve the full 200 mg dose of OMVOH.

Instruct Crohn's disease patients or caregivers to administer a 100 mg prefilled pen or prefilled syringe and a 200 mg prefilled pen or prefilled syringe in any order to achieve the full 300 mg dose of OMVOH.

Eli Lilly and Company, Indianapolis, IN 46285, USA
US License No. 1891

Copyright © 2023, 2025, Eli Lilly and Company. All rights reserved.

Pat.: www.lilly.com/patents

OMV-0009-USPI-20251104

Medication Guide
OMVOHTM (ahm-VOH)
(mirikizumab-mrkz)
injection, for intravenous or subcutaneous use

What is the most important information I should know about OMVOH?
OMVOH can cause serious side effects, including:

- Serious allergic reactions. OMVOH may cause serious allergic reactions that may need to be treated in a hospital and may be life-threatening. Stop using OMVOH and get emergency medical help right away if you develop any of the following symptoms of a serious allergic reaction:
  - fainting, dizziness, feeling lightheaded (low blood pressure)
  - swelling of your face, eyelids, lips, mouth, tongue, throat, or trouble swallowing
  - trouble breathing, throat tightening or wheezing
  - chest tightness
  - fast heartbeat or pounding in your chest (tachycardia)
  - severe itching, hives, or redness all over your body
  - sweating
- Infections. OMVOH may lower the ability of your immune system to fight infections and may increase your risk of infections. Your healthcare provider should not start treatment with OMVOH until your infection is gone.
  - Before starting your treatment with OMVOH, your healthcare provider should test you for tuberculosis (TB).
  - If your healthcare provider feels that you are at risk for TB, you may be treated with medicine for TB before you begin treatment with OMVOH.
  - Your healthcare provider should watch you closely for signs and symptoms of TB while you are being treated with OMVOH and after treatment.
  - Before starting OMVOH, tell your healthcare provider if you think you have an infection or have symptoms of an infection such as:
    - fever, sweating, or chills
    - muscle aches and pain
    - cough or shortness of breath
    - blood in your mucus (phlegm)
    - flu-like symptoms
    - headache
    - warm, red, or painful skin or sores on your body
    - diarrhea or stomach pain
    - weight loss
    - nausea or vomiting
    - pain during urination
  After starting OMVOH, tell your healthcare provider right away if you have any symptoms of an infection.
- Liver problems. OMVOH may cause liver problems. Your healthcare provider will do blood tests to check your liver enzyme and bilirubin levels before treatment, for at least 24 weeks during treatment, and possibly after treatment with OMVOH. Your healthcare provider may hold or stop your treatment if needed. Tell your healthcare provider right away if you develop any signs and symptoms of liver problems, including:
  - unexplained rash
  - nausea
  - vomiting
  - stomach-area (abdominal) pain
  - feeling tired
  - loss of appetite
  - yellowing of the skin or the whites of your eyes
  - dark urine

What is OMVOH?
OMVOH is a prescription medicine used to treat:

- adults with moderately to severely active ulcerative colitis
- adults with moderately to severely active Crohn's disease

It is not known if OMVOH is safe and effective in children.

Do not use OMVOH if you:

- are allergic to mirikizumab-mrkz or any of the ingredients in OMVOH. See the end of this Medication Guide for a complete list of ingredients in OMVOH.

Before you use OMVOH, tell your healthcare provider about all your medical conditions, including if you:

- have any of the conditions or symptoms listed in the section “What is the most important information I should know about OMVOH?”
- have recently received or are scheduled to receive any vaccinations. Medicines that affect your immune system may increase your risk of getting an infection after receiving live vaccines.
  - You should be brought up to date with all age required vaccines before starting treatment with OMVOH.
  - You should avoid receiving ‘live’ vaccines right before, during, or right after treatment with OMVOH. Tell your healthcare provider that you are taking OMVOH before receiving a vaccine.
- are pregnant, or plan to become pregnant. It is not known if OMVOH will harm your unborn baby. There will be a pregnancy registry to collect information about women who are exposed to OMVOH during pregnancy. If you become pregnant while taking OMVOH, you are encouraged to report your pregnancy to Eli Lilly and Company at 1-800-Lilly-Rx (1-800-545-5979).
- are breastfeeding or plan to breastfeed. It is not known if OMVOH passes into your breast milk. Talk to your healthcare provider about the best way to feed your baby while using OMVOH.

Tell your healthcare provider about all the medicines you take, including prescription and over-the-counter medicines, vitamins, and herbal supplements.

How should I use OMVOH?

- Use OMVOH exactly as your healthcare provider tells you to.
- You will receive your first 3 doses of OMVOH through a vein in your arm (intravenous infusion) in a healthcare facility by a healthcare provider every 4 weeks.
  - For ulcerative colitis, each infusion will last about 30 minutes.
  - For Crohn's disease, each infusion will last about 90 minutes.
- After your intravenous infusions, you will continue to receive OMVOH as an injection under the skin (subcutaneous injection) every 4 weeks as described below.
- See the detailed Instructions for Use that comes with OMVOH for information on how to prepare and inject a dose of OMVOH, and how to properly throw away (dispose of) used OMVOH prefilled pens or prefilled syringes.
- OMVOH comes as 2 different types of 1-time use devices:
  - a prefilled pen,
  - a prefilled syringe.
    Your healthcare provider will decide which type of device is best for you.
- For ulcerative colitis, you will need to inject one 200 mg/2 mL prefilled pen or 200 mg/2mL (100 mg/mL) prefilled syringe, or two 100 mg/mL prefilled pens or prefilled syringes for your full dose.
  - If 2 injections are required for your full dose, inject 1 OMVOH prefilled pen or prefilled syringe followed right away by the other OMVOH prefilled pen or prefilled syringe.
- For Crohn's disease, you will need 2 injections either with 2 prefilled pens or 2 prefilled syringes for your full dose.
  - You will need to inject one OMVOH 100 mg/mL prefilled pen or prefilled syringe and one 200 mg/2 mL prefilled pen or 200 mg/2 mL (100 mg/mL) prefilled syringe in any order.
- Injecting OMVOH under your skin:
  - OMVOH is intended for use under the guidance and supervision of your healthcare provider. If your healthcare provider decides that you or a caregiver may give your injections of OMVOH at home, you should receive training on the correct way to prepare and inject OMVOH. Do not try to inject OMVOH yourself until you or your caregiver have been shown how to inject OMVOH.
  - Inject OMVOH under the skin in your stomach area (abdomen), upper legs (thighs), or back of the upper arms.
  - Do not give an injection in an area that is tender, bruised, red, or hard.
  - Use a different injection site each time you use OMVOH.
- If you miss a dose of OMVOH, inject the missed dose as soon as possible. Then take your next dose in 4 weeks. If you have questions about how often you should use OMVOH, talk to your healthcare provider.

What are the possible side effects of OMVOH?
OMVOH can cause serious side effects, including:

- See “What is the most important information I should know about OMVOH?”

The most common side effects of OMVOH in people treated for ulcerative colitis include:

- upper respiratory infections
- injection site reactions

- joint pain
- headache

- rash
- herpes viral infections

The most common side effects of OMVOH in people treated for Crohn's disease include:

- upper respiratory infections
- injection site reactions

- elevated liver blood tests
- headache

- joint pain

Tell your healthcare provider if you have any side effect that bothers you or that does not go away.
These are not all the possible side effects of OMVOH. For more information, ask your healthcare provider or pharmacist.
Call your doctor for medical advice about side effects. You may report side effects to FDA at 1-800-FDA-1088.

How should I store OMVOH?

- In the original carton, store OMVOH prefilled pens and prefilled syringes in a refrigerator between 36°F to 46°F (2°C to 8°C).
- Do not freeze. Do not use OMVOH if it has been frozen.
- Do not shake.
- Keep OMVOH in the original carton to protect from light until the time of use.
- If needed, your prefilled pens or prefilled syringes may be stored at room temperature for up to 2 weeks in the original carton. Do not store above 86°F (30°C).
  - When OMVOH has been stored at room temperature, do not return it to the refrigerator.
- Do not use and throw away (dispose of) your prefilled pens and prefilled syringes if they:
  - have been frozen.
  - have been shaken.
  - have not been protected from light in the original carton.
  - have been stored at room temperature more than 2 weeks.

Keep OMVOH and all medicines out of the reach of children.

General information about the safe and effective use of OMVOH.
Medicines are sometimes prescribed for purposes other than those listed in a Medication Guide. Do not use OMVOH for a condition for which it was not prescribed. Do not give OMVOH to other people, even if they have the same symptoms that you have. It may harm them.
You can ask your pharmacist or healthcare provider for information about OMVOH that is written for health professionals.

What are the ingredients in OMVOH?
Active ingredient: mirikizumab-mrkz.
Inactive ingredients:

- Intravenous infusion: anhydrous citric acid, polysorbate 80, sodium chloride, sodium citrate, and Water for Injection. Some formulations may also contain histidine, L-histidine hydrochloride monohydrate, and mannitol.
- Subcutaneous injection: histidine, L-histidine hydrochloride monohydrate, mannitol, polysorbate 80, sodium chloride, and Water for Injection.

OMVOH prefilled pens and prefilled syringes are not made with dry natural rubber latex.
OMVOHTM is a trademark of Eli Lilly and Company.
Eli Lilly and Company, Indianapolis, IN 46285, USA
US License No. 1891
Copyright © 2023, 2025, Eli Lilly and Company. All rights reserved.
For more information, go to www.OMVOH.com or call 1-800-545-5979.

This Medication Guide has been approved by the U.S. Food and Drug Administration.

Revised: 10/2025

OMV-0005-MG-20251027

100 MG PREFILLED PEN INSTRUCTIONS FOR USE

INSTRUCTIONS FOR USE

OMVOHTM (ahm-VOH)

(mirikizumab-mrkz)

injection, for subcutaneous use

100 mg/mL prefilled Pens

This Instructions for Use contains information on how to inject OMVOH.

Before you use the OMVOH prefilled Pens, read and carefully follow all the step-by-step instructions. Two injections are required for a full dose.

Important information you need to know before injecting OMVOH:

- For injections under the skin (subcutaneous injection) only.
- Your healthcare provider should show you how to prepare and inject OMVOH using the prefilled Pen. Do not inject yourself or someone else until you have been shown how to inject OMVOH.
- Keep this Instructions for Use and read it as needed.
- 2 OMVOH injections are required for a full dose.
- Inject 1 OMVOH prefilled Pen followed right away by the other OMVOH prefilled Pen.
- Each OMVOH prefilled Pen is for 1-time use only.
- The OMVOH prefilled Pen contains glass parts. Handle it carefully. If you drop it on a hard surface do not use it. Use a new OMVOH prefilled Pen for your injection.
- Your healthcare provider may help you decide where on your body to inject your dose. You can also read the Choose your injection site section of these instructions to help you choose which area can work best for you.
- If you have vision or hearing problems, do not use OMVOH prefilled Pen without help from a caregiver.
- See Storing OMVOH Prefilled Pens for important storage information.

INSTRUCTIONS FOR USE

Before you use the OMVOH prefilled Pens, read and carefully follow all the step-by-step instructions.

Parts of the OMVOH prefilled Pen

Important:

- 2 OMVOH injections are required for a full dose.
- Inject 1 OMVOH prefilled Pen followed right away by the other OMVOH prefilled Pen.

2 injections are required for a full dose. Inject one prefilled Pen immediately followed by the other prefilled Pen.
Preparing to inject OMVOH
Take the prefilled Pens from the refrigerator | Take 2 OMVOH prefilled Pens from the refrigerator.
Take the prefilled Pens from the refrigerator | Leave the gray base caps on until you are ready to inject.
Take the prefilled Pens from the refrigerator | Leave the prefilled Pens at room temperature for 45 minutes before injecting.
Take the prefilled Pens from the refrigerator | Do not microwave the prefilled Pens, or run hot water over them, or leave them in direct sunlight.
Take the prefilled Pens from the refrigerator | Do not shake the prefilled Pens.
Gather supplies | Supplies:; - 2 alcohol wipes - 2 cotton balls or pieces of gauze - 1 sharps container (see Throwing away (disposing of) OMVOH Prefilled Pens)
Inspect the prefilled Pens and the medicine Expiration date | Make sure you have the right medicine. The medicine inside should be clear. It may be colorless to slightly yellow to slightly brown. Do not use the prefilled Pens and throw away (dispose of) as directed by your healthcare provider or pharmacist if:; - one or both prefilled Pens look damaged - the medicine is cloudy, is discolored, or has particles - the expiration date printed on the label has passed - the medicine is frozen
Prepare for injection | Wash your hands with soap and water before you inject OMVOH.
Choose your injection site | Your healthcare provider can help you choose the injection site that is best for you.
 | - You or another person may inject the medicine into your stomach area (abdomen). Do not inject within 2 inches of the belly button (navel). - You or another person may inject the medicine in the front of your thighs. This area should be at least 2 inches above the knee and 2 inches below the groin. - Another person may give you the injection in the back of your upper arm. - Do not inject in the exact same spot every time. For example, if your first injection was in your abdomen, your second injection (to complete a full dose) should be in another spot in your abdomen, or upper arm, or thigh. - Do not inject into areas where the skin is tender, bruised, red, or hard.; Clean the injection sites with an alcohol wipe. Let the injection sites dry before you inject the medicine.

Injecting OMVOH
1 | Uncap the prefilled Pen
1 |  | Make sure the prefilled Pen is locked. Leave the gray base cap on until you are ready to inject.
1 | - Twist off the gray base cap and throw it away in your household trash. - Do not put the gray base cap back on. This could damage the needle. - Do not touch the needle.
2 | Place and unlock
2 | - Place and hold the clear base flat and firmly against the skin.
 |  | Keep the clear base on the skin, then turn the lock ring to the unlock position.
3 | Press and hold for up to 10 seconds
3 | - Press and hold the blue injection button. You will hear a loud click (injection started). - Keep holding the clear base firmly against the skin. You will hear a second loud click in about 10 seconds after the first one (injection completed). - You will know the injection is complete when the gray plunger is visible. - Remove the prefilled Pen from the skin. - If you have bleeding at the injection site, press a cotton ball or gauze over the injection site. - Do not rub the injection site, as this may cause bruising.
3 | - Press and hold the blue injection button. You will hear a loud click (injection started). - Keep holding the clear base firmly against the skin. You will hear a second loud click in about 10 seconds after the first one (injection completed). - You will know the injection is complete when the gray plunger is visible. - Remove the prefilled Pen from the skin. - If you have bleeding at the injection site, press a cotton ball or gauze over the injection site. - Do not rub the injection site, as this may cause bruising.
4 | Inject the second prefilled Pen; - Choose a new injection site at least 2 inches away and clean it. - With your second prefilled Pen, repeat steps 1 to 3 right away after your first injection. - You must inject 2 prefilled Pens to complete your full 200 mg dose.
 | Inject the second prefilled Pen; - Choose a new injection site at least 2 inches away and clean it. - With your second prefilled Pen, repeat steps 1 to 3 right away after your first injection. - You must inject 2 prefilled Pens to complete your full 200 mg dose.
 | Inject the second prefilled Pen; - Choose a new injection site at least 2 inches away and clean it. - With your second prefilled Pen, repeat steps 1 to 3 right away after your first injection. - You must inject 2 prefilled Pens to complete your full 200 mg dose.

Throwing away (disposing of) OMVOH Prefilled Pens

Throw away the used prefilled Pens

- Put the used OMVOH prefilled Pens in an FDA-cleared sharps disposal container right away after use. Do not throw away (dispose of) the OMVOH prefilled Pens in your household trash.

- If you do not have an FDA-cleared sharps disposal container, you may use a household container that is:
  - made of a heavy-duty plastic,
  - can be closed with a tight-fitting, puncture-resistant lid, without sharps being able to come out,
  - upright and stable during use,
  - leak-resistant, and
  - properly labeled to warn of hazardous waste inside the container.
- When your sharps disposal container is almost full, you will need to follow your community guidelines for the right way to dispose of your sharps disposal container. There may be local laws about how you should throw away needles and syringes.
- For more information about safe sharps disposal, and for specific information about sharps disposal in the state you live in, go to the FDA's website at: http://www.fda.gov/safesharpsdisposal.
- Do not recycle your used sharps disposal container.

Commonly asked questions
Q. | What if I let my prefilled Pen warm up for longer than 45 minutes before injecting?
A. | Your prefilled Pen can stay at room temperature up to 86°F (30°C) for up to 2 weeks.
Q. | What if I see air bubbles in the prefilled Pen?
A. | It is normal to have air bubbles in the prefilled Pen. They will not harm you or affect your dose.
Q. | What if there is a drop of liquid on the tip of the needle when I remove the gray base cap?
A. | It is okay to see a drop of liquid on the tip of the needle. This will not harm you or affect your dose.
Q. | What if I unlocked the prefilled Pen and pressed the blue injection button before I twisted off the gray base cap?
A. | Do not remove the gray base cap. Throw away (dispose of) the prefilled Pen and get a new one.
Q. | Do I need to hold the blue injection button down until the injection is complete?
A. | You do not need to hold the blue injection button down, but it may help you keep the prefilled Pen steady and firm against your skin.
Q. | What if the needle did not retract after my injection?
A. | Do not touch the needle or replace the gray base cap. Store the prefilled Pen in a safe place to avoid an accidental needlestick and contact 1-800-Lilly-Rx (1-800-545-5979) for instructions on how to return the prefilled Pen.
Q. | What if there is a drop of liquid or blood on my skin after my injection?
A. | This is normal. Press a cotton ball or gauze over the injection site. Do not rub the injection site.
Q. | What if I heard more than 2 clicks during my injection – 2 loud clicks and a soft one. Did I get my complete injection?
A. | Some patients may hear a soft click right before the second loud click. That is the normal operation of the prefilled Pen. Do not remove the prefilled Pen from your skin until you hear the second loud click.
Q. | How can I tell if my injection is complete?
A. | After you press the blue injection button, you will hear 2 loud clicks. The second loud click tells you that your injection is complete. You will also see the gray plunger at the top of the clear base.
If you have more questions about how to use the OMVOH prefilled Pen:
 | - Call your healthcare provider - Call 1-800-Lilly-Rx (1-800-545-5979) - Visit www.OMVOH.com |  | Scan this code to launch www.OMVOH.com
 | - Call your healthcare provider - Call 1-800-Lilly-Rx (1-800-545-5979) - Visit www.OMVOH.com |  | Scan this code to launch www.OMVOH.com
 | - Call your healthcare provider - Call 1-800-Lilly-Rx (1-800-545-5979) - Visit www.OMVOH.com |  | Scan this code to launch www.OMVOH.com

Storing OMVOH Prefilled Pens

Refrigeration

- In the original carton, store your prefilled Pens in the refrigerator between 36ºF to 46ºF (2ºC to 8ºC) until the expiration date.

- Do not freeze. Do not use OMVOH if it has been frozen.

Room temperature

- If needed, your prefilled Pens may be stored at room temperature for up to 2 weeks in the original carton. Do not store above 86°F (30°C).
- When OMVOH has been stored at room temperature, do not return it to the refrigerator.
- Throw away (dispose of) OMVOH if not used within 2 weeks at room temperature.

- Protect your prefilled Pens from light until use.

Do not use the prefilled Pens and throw away (see Throwing away (disposing of) OMVOH Prefilled Pens) if they have been:

- Frozen
- microwaved
- warmed with hot water

- left in direct sunlight
- shaken

- Keep OMVOH and all medicines out of the reach of children.

Read the Medication Guide for OMVOH inside this box to learn more about your medicine.

This Instructions for Use has been approved by the U.S. Food and Drug Administration.

Manufactured by:

Eli Lilly and Company

Indianapolis, IN 46285, USA

US License Number 1891

OMVOH™ is a trademark of Eli Lilly and Company.

Copyright © 2023, 2025, Eli Lilly and Company. All rights reserved.

Revised: October 2025

The OMVOH prefilled Pen meets the current dose accuracy and functional requirements of ISO 11608-1 and 11608-5.

OMV-0005-IFU-PEN-20251023

100 MG PREFILLED SYRINGE INSTRUCTIONS FOR USE

INSTRUCTIONS FOR USE

OMVOHTM (ahm-VOH)

(mirikizumab-mrkz)

injection, for subcutaneous use

100 mg/mL prefilled syringe

This Instructions for Use contains information on how to inject OMVOH.

Before you use the OMVOH prefilled syringes, read and carefully follow all the step-by-step instructions. Two injections are required for a full dose.

Important information you need to know before injecting OMVOH:

- For injection under the skin (subcutaneous injection) only.
- Your healthcare provider should show you how to prepare and inject OMVOH using the prefilled syringes. Do not inject yourself or someone else until you have been shown how to inject OMVOH.
- Keep this Instructions for Use and read it as needed.
- 2 OMVOH injections are required for a full dose.
- Inject 1 OMVOH prefilled syringe followed right away by the other OMVOH prefilled syringe.
- Each OMVOH prefilled syringe is for 1-time use only. Do not share or reuse your OMVOH prefilled syringe. You may give or get an infection.
- The OMVOH prefilled syringes contain glass parts. Handle it carefully. If you drop it on a hard surface, do not use it. Use a new OMVOH prefilled syringe for your injection.
- Your healthcare provider may help you decide where on your body to inject your dose. You can also read the Choose your injection site section of these instructions to help you choose which area can work best for you.
- If you have vision problems, do not use OMVOH prefilled syringes without help from a caregiver.
- See Storing OMVOH prefilled syringes for important storage information.

INSTRUCTIONS FOR USE

Before you use OMVOH prefilled syringes, read and carefully follow all the step-by-step instructions.

Parts of the OMVOH prefilled syringe

Top

Important:

- 2 OMVOH injections are required for a full dose.
- Inject 1 OMVOH prefilled syringe followed right away by the other OMVOH prefilled syringe.

2 injections are required for a full dose. Inject one prefilled syringe immediately followed by the other prefilled syringe.

Preparing to inject OMVOH
Take the prefilled syringes from the refrigerator | Take 2 OMVOH prefilled syringes from the refrigerator.
Take the prefilled syringes from the refrigerator | Leave the needle caps on until you are ready to inject.
Take the prefilled syringes from the refrigerator | Leave the prefilled syringes at room temperature for 45 minutes before injecting.
Take the prefilled syringes from the refrigerator | Do not microwave the prefilled syringes, or run hot water over them, or leave them in direct sunlight.
Take the prefilled syringes from the refrigerator | Do not shake the prefilled syringes.
Gather supplies | Supplies:; - 2 alcohol wipes - 2 cotton balls or pieces of gauze - 1 sharps container (see Throwing away (disposing of) OMVOH prefilled syringes)
Inspect the prefilled syringes and the medicine Expiration date | Make sure you have the right medicine. The medicine inside should be clear. It may be colorless to slightly yellow to slightly brown.
Inspect the prefilled syringes and the medicine Expiration date | Do not use the prefilled syringes and throw away (dispose of) as directed by your healthcare provider or pharmacist if:; - one or both prefilled syringes look damaged - the medicine is cloudy, is discolored, or has particles - the expiration date printed on the label has passed - the medicine is frozen
Prepare for injection | Wash your hands with soap and water before you inject OMVOH.
Choose your injection site | Your healthcare provider can help you choose the injection site that is best for you.; - You or another person may inject the medicine into your stomach area (abdomen). Do not inject within 2 inches of the belly button (navel). - You or another person may inject the medicine in the front of your thighs. This area should be at least 2 inches above the knee and 2 inches below the groin. - Another person may give you the injection in the back of your upper arm. - Do not inject in the exact same spot every time. For example, if your first injection was in your abdomen, your second injection (to complete a full dose) should be in another spot in your abdomen. - Do not inject into areas where the skin is tender, bruised, red, or hard.
 | Your healthcare provider can help you choose the injection site that is best for you.; - You or another person may inject the medicine into your stomach area (abdomen). Do not inject within 2 inches of the belly button (navel). - You or another person may inject the medicine in the front of your thighs. This area should be at least 2 inches above the knee and 2 inches below the groin. - Another person may give you the injection in the back of your upper arm. - Do not inject in the exact same spot every time. For example, if your first injection was in your abdomen, your second injection (to complete a full dose) should be in another spot in your abdomen. - Do not inject into areas where the skin is tender, bruised, red, or hard.
 | Clean the injection sites with an alcohol wipe. Let the injection sites dry before you inject the medicine.

Injecting OMVOH
1 | Uncap the prefilled syringe
1 | Leave the needle cap on until you are ready to inject.
1 | - Pull the needle cap off and throw it away in your household trash. - Do not put the needle cap back on. You could damage the needle or stick yourself by accident. - Do not touch the needle.
2 | Insert
 | - Gently pinch and hold a fold of skin where you will inject. - Insert the needle at a 45-degree angle.
 | - Gently pinch and hold a fold of skin where you will inject. - Insert the needle at a 45-degree angle.
3 | Inject
3 | - Slowly push on the blue thumb pad to push the plunger all the way in until all the medicine is injected. - The gray syringe plunger should be pushed all the way to the needle end of the syringe. - You should see the blue plunger rod show through the syringe body when the injection is complete as shown. - Remove the needle from your skin and gently let go of your skin. - If you have bleeding at the injection site, press a cotton ball or gauze over the injection site. - Do not rub the injection site, as this may cause bruising. - Do not put the needle cap back on the prefilled syringe.
3 | - Slowly push on the blue thumb pad to push the plunger all the way in until all the medicine is injected. - The gray syringe plunger should be pushed all the way to the needle end of the syringe. - You should see the blue plunger rod show through the syringe body when the injection is complete as shown. - Remove the needle from your skin and gently let go of your skin. - If you have bleeding at the injection site, press a cotton ball or gauze over the injection site. - Do not rub the injection site, as this may cause bruising. - Do not put the needle cap back on the prefilled syringe. |  | Blue plunger rod Gray syringe plunger

4 | Inject the second prefilled syringe; - Choose a new injection site at least 2 inches away and clean it. - With your second prefilled syringe, repeat steps 1 to 3 right away after your first injection - You must inject 2 prefilled syringes to complete your full 200 mg dose.
 | Inject the second prefilled syringe; - Choose a new injection site at least 2 inches away and clean it. - With your second prefilled syringe, repeat steps 1 to 3 right away after your first injection - You must inject 2 prefilled syringes to complete your full 200 mg dose.
 | Inject the second prefilled syringe; - Choose a new injection site at least 2 inches away and clean it. - With your second prefilled syringe, repeat steps 1 to 3 right away after your first injection - You must inject 2 prefilled syringes to complete your full 200 mg dose.

Throwing away (disposing of) OMVOH prefilled syringes

Throw away the used prefilled syringes

- Put the used OMVOH prefilled syringes in an FDA-cleared sharps disposal container right away after use. Do not throw away (dispose of) the OMVOH prefilled syringes in your household trash.

- If you do not have an FDA-cleared sharps disposal container, you may use a household container that is:
  - made of a heavy-duty plastic,
  - can be closed with a tight-fitting, puncture-resistant lid, without sharps being able to come out,
  - upright and stable during use,
  - leak-resistant, and
  - properly labeled to warn of hazardous waste inside the container.
- When your sharps disposal container is almost full, you will need to follow your community guidelines for the right way to dispose of your sharps disposal container. There may be state or local laws about how you should throw away needles and syringes.
- For more information about safe sharps disposal, and for specific information about sharps disposal in the state you live in, go to the FDA's website at: http://www.fda.gov/safesharpsdisposal.
- Do not recycle your used sharps disposal container.

Commonly asked questions
Q. | What if I let my OMVOH prefilled syringe warm up for longer than 45 minutes before injecting?
A. | Your prefilled syringe can stay at room temperature up to 86°F (30°C) for up to 2 weeks.
Q. | What if I see air bubbles in the OMVOH prefilled syringe?
A. | It is normal to have air bubbles in the prefilled syringe. They will not harm you or affect your dose.
Q. | What if there is a drop of liquid on the tip of the needle when I remove the needle cap?
A. | It is okay to see a drop of liquid on the tip of the needle. This will not harm you or affect your dose.
Q. | What if I cannot push in the plunger?
A. | If the plunger is stuck or damaged:
 | - Do not continue to use the prefilled syringe - Remove the needle from your skin - Throw away (dispose of) the prefilled syringe and get a new one
 | - Do not continue to use the prefilled syringe - Remove the needle from your skin - Throw away (dispose of) the prefilled syringe and get a new one
 | - Do not continue to use the prefilled syringe - Remove the needle from your skin - Throw away (dispose of) the prefilled syringe and get a new one
Q. | What if there is a drop of liquid or blood on my skin after my injection?
A. | This is normal. Press a cotton ball or gauze over the injection site. Do not rub the injection site.
Q. | How can I tell if my injection is complete?
A. | When your injection is complete:
 | - The blue plunger rod should show through the body of the syringe. - The gray syringe plunger should be pushed all the way to the needle end of the syringe.
If you have more questions about how to use the OMVOH prefilled syringe:
 | - Call your healthcare provider - Call 1-800-LillyRx (1-800-545-5979) - Visit www.OMVOH.com |  | Scan this code to launch www.OMVOH.com
 | - Call your healthcare provider - Call 1-800-LillyRx (1-800-545-5979) - Visit www.OMVOH.com |  | Scan this code to launch www.OMVOH.com

Storing OMVOH prefilled syringes

- Store your prefilled syringes in the refrigerator between 36ºF to 46ºF (2ºC to 8ºC).
- If needed, your prefilled syringes may be stored at room temperature for up to 2 weeks. Do not store above 86°F (30°C). Throw away (dispose of) OMVOH if not used within 2 weeks at room temperature. When OMVOH has been stored at room temperature, do not return it to the refrigerator.
- Do not freeze your prefilled syringes.
- Store your prefilled syringes in the original carton to protect from light until use.
- Do not microwave your prefilled syringes, or run hot water over them, or leave them in direct sunlight.
- Do not shake your prefilled syringes.
- Throw away (dispose of) your prefilled syringes if any of the above conditions are not followed.
- Keep your prefilled syringes and all medicines out of the sight and reach of children.

Read the Medication Guide for OMVOH inside this box to learn more about your medicine.

This Instructions for Use has been approved by the U.S. Food and Drug Administration.

Manufactured by:
Eli Lilly and Company
Indianapolis, IN 46285, USA
US License Number 1891

OMVOHTM is a trademark of Eli Lilly and Company.

Copyright © 2024, 2025, Eli Lilly and Company. All rights reserved.

Revised: October 2025

OMV-0003-IFU-PFS-20251023

100 MG + 200 MG PREFILLED PEN INSTRUCTIONS FOR USE

INSTRUCTIONS FOR USE

OMVOHTM (ahm-voh)

(mirikizumab-mrkz)

injection, for subcutaneous use

Prefilled Pens

One 200 mg/2 mL Prefilled Pen and one 100 mg/mL Prefilled Pen for a full dose of 300 mg

This Instructions for Use contains information on how to inject OMVOH.

Before you use the OMVOH prefilled Pens, read and carefully follow all the step-by-step instructions.

Important information you need to know before injecting OMVOH

- 2 OMVOH injections, using the provided 100 mg/mL and 200 mg/2 mL prefilled Pens, are required for a full 300 mg dose.
- The prefilled Pens may be used in any order.
- Inject 1 OMVOH prefilled Pen followed right away by the other OMVOH prefilled Pen.

- Your healthcare provider should show you how to prepare and inject OMVOH using the prefilled Pens. Do not inject yourself or someone else until you have been shown how to inject OMVOH.
- Keep this Instructions for Use and read it as needed.
- Each OMVOH prefilled Pen is for one-time use only.
- The OMVOH prefilled Pen contains glass parts. Handle it carefully. If you drop it on a hard surface, do not use it. Use a new OMVOH prefilled Pen for your injection.
- Your healthcare provider can help you decide where on your body to inject your dose. Read the Choose and clean your injection sites section of these instructions to help you choose which area can work best for you.
- If you have vision or hearing problems, do not use OMVOH prefilled Pens without help from a caregiver.
- See Storing OMVOH Prefilled Pens for important storage information.

INSTRUCTIONS FOR USE

Before you use the OMVOH prefilled Pens, read and carefully follow all the step-by-step instructions.

2 Prefilled Pens = full 300 mg dose

After your first injection, choose a new injection site at least 2 inches (5 centimeters) away and clean it.

With your second prefilled Pen, repeat steps 1 to 3 right away after your first injection.

You must inject 2 prefilled Pens to complete your full 300 mg dose.

Parts of the OMVOH Prefilled Pens

Inject both prefilled Pens in any order for a full 300 mg dose.

The 200 mg/2 mL prefilled Pen is larger than the 100 mg/mL prefilled Pen.

Preparing to inject OMVOH

Gather supplies

- a carton containing 2 OMVOH prefilled Pens from the refrigerator
- 2 alcohol wipes

- 2 cotton balls
- sharps disposal container

Inspect the prefilled Pens and the medicine

Remove both prefilled Pens from the carton.

Make sure you have the right medicine.

The medicine inside should be clear. It may be colorless to slightly yellow to slightly brown.

Do not use the prefilled Pens (see Throwing away (disposing of) OMVOH Prefilled Pens) if:

- one or both prefilled Pens looks damaged
- the medicine is cloudy, discolored, or has particles
- the expiration date printed on the label has passed
- the medicine is or has been frozen.

Wait 45 minutes

Do not warm up the prefilled Pens with a microwave, hot water, or direct sunlight.

With the gray base cap on, allow the prefilled Pens to warm up to room temperature for 45 minutes before injecting.

Choose and clean your injection sites

Your healthcare provider can help you choose the injection sites that are best for you. Clean the injection sites with an alcohol wipe and let them dry.

 | You or another person may inject into these areas. | Do not inject into areas where the skin is tender, bruised, red, or hard.; - Stomach area (abdomen) At least 2 inches away from the belly button (navel). - Front of thigh At least 2 inches above the knee and 2 inches below the groin.
 | Another person should inject into this area. | - Back of upper arm Another person should inject into the back of your upper arm. Injections should be at least 2 inches apart.

Injecting OMVOH

1. Uncap the first prefilled Pen (the prefilled Pens may be used in any order)

Make sure the prefilled Pen is locked.

Twist off the gray base cap and throw the cap away in the trash when you are ready to inject.
Do not put the gray base cap back on –
this could damage the needle.
Do not touch the needle inside the clear base.

2. Place and unlock

Clear base

Place and hold the clear base flat against the skin.
Keep the clear base on the skin, then turn the lock ring to the unlock position.

3. Press and hold for 15 seconds

Press and Hold the blue injection button and listen for 2 loud clicks:

- first click = injection started
- second click = injection completed

The injection may take up to 15 seconds.

You will know the injection is complete when the gray plunger is visible.

Remove the prefilled Pen from the skin.
If you have bleeding at the injection site, press a cotton ball over the injection site.
Do not rub the injection site.

4. Inject the second prefilled Pen

Choose a new injection site at least 2 inches away and clean it.

With your second prefilled Pen, repeat steps 1 to 3 right away after your first injection.

You must inject 2 prefilled Pens to complete your full 300 mg dose.

Throwing away (disposing of) OMVOH Prefilled Pens

Throw away both used prefilled Pens

Put the used OMVOH prefilled Pens in an FDA-cleared sharps disposal container right away after use.
Do not throw away (dispose of) the OMVOH prefilled Pens in your household trash.
Do not recycle your sharps disposal container.

For more information, see Used OMVOH prefilled Pen disposal.

Storing OMVOH Prefilled Pens

Refrigeration

- In the original carton, store your prefilled pens in the refrigerator between 36°F to 46°F (2°C to 8°C) until the expiration date.
- Do not freeze. Do not use OMVOH if it has been frozen.

Room Temperature

- If needed, your prefilled Pens may be stored at room temperature for up to 2 weeks in the original carton. Do not store above 86°F (30°C).
- When OMVOH has been stored at room temperature, do not return it to the refrigerator.
- Throw away (dispose of) OMVOH if not used within 2 weeks at room temperature.
- Protect your prefilled Pens from light until use.

Do not use the prefilled Pens and throw away (see Throwing away (disposing of) OMVOH Prefilled Pens) if they have been:

- frozen
- microwaved
- warmed with hot water

- left in direct sunlight
- shaken

Keep OMVOH and all medicines out of the reach of children.

Commonly asked questions

Q. | The prefilled Pens are different sizes. Should I take one before the other?
A. | You can inject the prefilled Pens in any order. Inject both prefilled Pens for a full 300 mg dose.
Q. | What if I see air bubbles in the prefilled Pens?
A. | Air bubbles are normal. They will not harm you or affect your dose.
Q. | What if there is a drop of liquid on the tip of the needle when I remove the gray base cap?
A. | A drop of liquid on the tip of the needle is normal. This will not harm you or affect your dose. Do not touch the needle.
Q. | What if I unlock the prefilled Pen and press the blue injection button before twisting off the gray base cap?
A. | Do not remove the gray base cap. Throw away (dispose of) the prefilled Pen and get a new one.
Q. | Do I need to hold the blue injection button down until the injection is complete?
A. | You do not need to hold the blue injection button down, but it may help you keep the prefilled Pen steady against your skin.
Q. | What if the needle did not retract after my injection?
A. | Do not touch the needle or replace the gray base cap. Store the prefilled Pen in a safe place to avoid an accidental needlestick and contact 1-800-Lilly-Rx (1-800-545-5979) for instructions on how to return the prefilled Pen.
Q. | What if there is a drop of liquid or blood on my skin after my injection?
A. | This is normal. Press a cotton ball over the injection site. Do not rub the injection site.
Q. | How can I tell if my injection is complete?
A. | After you press the blue injection button, you will hear 2 loud clicks. The second loud click tells you that your injection is complete. You will also see the gray plunger at the top of the clear base. The injection may take up to 15 seconds.
Q. | What if I remove the prefilled Pen before the second loud click or before the gray plunger stops moving?
A. | You may not have received your full dose. Do not give another injection. Call your healthcare provider for help.
Q. | What if I heard more than 2 clicks during my injection – 2 loud clicks and 1 soft one. Did I get my complete injection?
A. | Some people may hear a soft click right before the second loud click. That is the normal operation of the prefilled Pen. Do not remove the prefilled Pen from your skin until you hear the second loud click.

Additional Information:

If you have more questions about how to use the OMVOH prefilled Pens:

- Call your healthcare provider - Call 1-800-Lilly-Rx (1-800-545-5979) - Visit www.OMVOH.com |  | Scan this code to launch www.OMVOH.COM

Used OMVOH Prefilled Pen disposal

Put the used OMVOH prefilled Pens in an FDA-cleared sharps disposal container right away after use. Do not throw away (dispose of) the OMVOH prefilled Pens in your household trash.

If you do not have an FDA-cleared sharps disposal container, you may use a household container that is:

- made of a heavy-duty plastic,
- can be closed with a tight-fitting, puncture-resistant lid, without sharps being able to come out,
- upright and stable during use,
- leak-resistant, and
- properly labeled to warn of hazardous waste inside the container.

When your sharps disposal container is almost full, you will need to follow your community guidelines for the right way to dispose of your sharps disposal container.

There may be state or local laws about how you should throw away needles and syringes.

For more information about safe sharps disposal, and for specific information about sharps disposal in the state you live in, go to the FDA's website at: http://www.fda.gov/safesharpsdisposal.

Do not recycle your used sharps disposal container.

Read the Medication Guide for OMVOH inside this box to learn more about your medicine.

Manufactured by:
Eli Lilly and Company
Indianapolis, IN 46285, USA
US License Number 1891

OMVOHTM is a trademark of Eli Lilly and Company.

Copyright © 2025, Eli Lilly and Company. All rights reserved.

This Instructions for Use has been approved by the U.S. Food and Drug Administration. Approved: January 2025

The OMVOH prefilled Pen meets the current dose accuracy and functional requirements of ISO 11608-1 and 11608-5.

OMV-0001-300MG-PEN-IFU-20250115

100 MG + 200 MG PREFILLED SYRINGE INSTRUCTIONS FOR USE

INSTRUCTIONS FOR USE

OMVOHTM (ahm-voh)

(mirikizumab-mrkz)

injection, for subcutaneous use

Prefilled Syringes

One 200 mg/2 mL (100 mg/mL) Prefilled Syringe and One 100 mg/mL Prefilled Syringe for a Full Dose of 300 mg.

This Instructions for Use contains information on how to inject OMVOH.

Before you use the OMVOH prefilled Syringes, read and carefully follow all the step-by-step instructions.

Important information you need to know before injecting OMVOH

- 2 OMVOH injections, using the provided 100 mg/mL and 200 mg/2 mL (100 mg/mL) prefilled Syringes, are required for a full 300 mg dose.
- The prefilled Syringes may be used in any order.
- Inject 1 OMVOH prefilled Syringe followed right away by the other OMVOH prefilled Syringe.

- Your healthcare provider should show you how to prepare and inject OMVOH using the prefilled Syringes. Do not inject yourself or someone else until you have been shown how to inject OMVOH.
- Keep this Instructions for Use and read it as needed.
- Each OMVOH prefilled Syringe is for one-time use only.
- Your healthcare provider can help you decide where on your body to inject your dose. Read the Choose and clean your injection sites section of these instructions to help you choose which area can work best for you.
- If you have vision problems, do not use OMVOH prefilled Syringes without help from a caregiver.
- See Storing OMVOH prefilled Syringes for important storage information.

INSTRUCTIONS FOR USE

Before you use the OMVOH prefilled Syringes, read and carefully follow all the step-by-step instructions.

2 Prefilled Syringes = full 300 mg dose

After your first injection, choose a new injection site at least 2 inches away and clean it.

With your second prefilled Syringe, repeat steps 1 to 3 right away after your first injection.

You must inject 2 prefilled Syringes to complete your full 300 mg dose.

Parts of the OMVOH prefilled Syringes

Inject both prefilled Syringes in any order for a full 300 mg dose.

The 200 mg/2 mL (100 mg/mL) prefilled Syringe is larger than the 100 mg/mL prefilled Syringe.

Preparing to inject OMVOH

Gather supplies

- a carton containing 2 OMVOH prefilled Syringes from the refrigerator
- 2 alcohol wipes

- 2 cotton balls
- sharps disposal container

Inspect the prefilled Syringes and the medicine

Remove both prefilled Syringes from the carton.

Make sure you have the right medicine.

The medicine inside should be clear. It may be colorless to slightly yellow to slightly brown.

Do not use the prefilled Syringes (see Throwing away (disposing of) OMVOH Prefilled Syringes) if:

- one or both prefilled Syringes looks damaged
- the medicine is cloudy, discolored, or has particles
- the expiration date printed on the label has passed
- the medicine is or has been frozen.

Wait 45 minutes

Do not warm up the prefilled Syringes with a microwave, hot water, or direct sunlight.

With the needle cap on, allow the prefilled Syringes to warm up to room temperature for 45 minutes before injecting.

Choose and clean your injection sites

Your healthcare provider can help you choose the injection sites that are best for you. Clean the injection sites with an alcohol wipe and let them dry.

 | You or another person may inject into these areas. | Do not inject into areas where the skin is tender, bruised, red, or hard.; - Stomach area (abdomen) At least 2 inches away from the belly button (navel). - Front of thigh At least 2 inches above the knee and 2 inches below the groin.
 | Another person should inject into this area. | - Back of upper arm Another person should inject into the back of your upper arm.; Injections should be at least 2 inches apart.

Injecting OMVOH

1. Uncap the first prefilled Syringe (the prefilled Syringes may be used in any order)

Hold the prefilled syringe body and pull off the needle cap when you are ready to inject. Throw away the needle cap in the trash.
Do not put the needle cap back on —
this could damage the needle.
Do not touch the needle.

2. Pinch the injection site and insert the needle

Gently pinch and hold a fold of skin where you will inject.
Insert the needle at a 45-degree angle.
Gently let go of the skin while keeping the needle in place.

3. Inject the medicine

Slowly push on the thumb pad to push the blue plunger rod all the way in until all the medicine is injected.
The gray syringe plunger should be pushed all the way to the needle end of the prefilled Syringe.

You should see the blue plunger rod show through the prefilled Syringe body when the injection is complete as shown.
Remove the needle from your skin.
Do not put the needle cap back on the prefilled Syringe.

If you have bleeding at the injection site, press a cotton ball over the injection site. Do not rub the injection site.

4. Inject the second prefilled Syringe

Choose a new injection site at least 2 inches away and clean it.

With your second prefilled Syringe, repeat steps 1 to 3 right away after your first injection.

You must inject 2 prefilled Syringes to complete your full 300 mg dose.

Throwing away (disposing of) OMVOH Prefilled Syringes

Throw away both used prefilled Syringes

Put the used OMVOH prefilled Syringes in an FDA-cleared sharps disposal container right away after use.
Do not throw away (dispose of) the OMVOH prefilled Syringes in your household trash.
Do not recycle your used sharps disposal container.

For more information, see Used OMVOH prefilled Syringe disposal.

Storing OMVOH Prefilled Syringes

Refrigeration

- In the original carton, store your prefilled Syringes in the refrigerator between 36°F to 46°F (2°C to 8°C) until the expiration date.
- Do not freeze. Do not use OMVOH if it has been frozen.

Room Temperature

- If needed, your prefilled Syringes may be stored at room temperature for up to 2 weeks in the original carton. Do not store above 86°F (30°C).
- When OMVOH has been stored at room temperature, do not return it to the refrigerator.
- Throw away (dispose of) OMVOH if not used within 2 weeks at room temperature.
- Protect your prefilled Syringes from light until use.

Do not use the prefilled Syringes and throw away (see Throwing away (disposing of) OMVOH Prefilled Syringes) if they have been:

- frozen
- microwaved
- warmed with hot water

- left in direct sunlight
- shaken

Keep OMVOH and all medicines out of the reach of children.

Commonly asked questions

Q. | The prefilled Syringes are different sizes. Should I take one before the other?
A. | You can inject the prefilled Syringes in any order. Inject both prefilled Syringes for a full 300 mg dose.
Q. | What if I see air bubbles in the prefilled Syringes?
A. | Air bubbles are normal. They will not harm you or affect your dose.
Q. | What if there is a drop of liquid on the tip of the needle when I remove the needle cap?
A. | A drop of liquid on the tip of the needle is normal. This will not harm you or affect your dose. Do not touch the needle.
Q. | What if I cannot push in the plunger?
A. | If the plunger is stuck or damaged: • Do not continue to use the prefilled Syringe; - Remove the needle from your skin - Dispose of the prefilled Syringe and get a new one
Q. | What if there is a drop of liquid or blood on my skin after my injection?
A. | This is normal. Press a cotton ball over the injection site. Do not rub the injection site.
Q. | How can I tell if my injection is complete?
A. | When your injection is complete:; - The blue plunger rod should show through the body of the prefilled Syringe. - The gray syringe plunger should be pushed all the way to the needle end of the prefilled Syringe.

Additional Information:

If you have more questions about how to use the OMVOH prefilled Syringes:

- Call your healthcare provider - Call 1-800-Lilly-Rx (1-800-545-5979) - Visit www.OMVOH.com |  | Scan this code to launch www.OMVOH.COM

Used OMVOH Prefilled Syringe disposal

Put the used OMVOH prefilled Syringes in an FDA-cleared sharps disposal container right away after use. Do not throw away (dispose of) the OMVOH prefilled Syringes in your household trash.

If you do not have an FDA-cleared sharps disposal container, you may use a household container that is:

- made of a heavy-duty plastic,
- can be closed with a tight-fitting, puncture-resistant lid, without sharps being able to come out,
- upright and stable during use,
- leak-resistant, and
- properly labeled to warn of hazardous waste inside the container.

When your sharps disposal container is almost full, you will need to follow your community guidelines for the right way to dispose of your sharps disposal container.

There may be state or local laws about how you should throw away needles and syringes.

For more information about safe sharps disposal, and for specific information about sharps disposal in the state you live in, go to the FDA's website at: http://www.fda.gov/safesharpsdisposal.

Do not recycle your used sharps disposal container.

Read the Medication Guide for OMVOH inside this box to learn more about your medicine.

Manufactured by:
Eli Lilly and Company
Indianapolis, IN 46285, USA
US License Number 1891

OMVOHTM is a trademark of Eli Lilly and Company.

Copyright © 2025, Eli Lilly and Company. All rights reserved.

This Instructions for Use has been approved by the U.S. Food and Drug Administration.

Approved: January 2025

OMV-0001-300MG-PFS-IFU-20250115

200 MG PREFILLED PEN INSTRUCTIONS FOR USE

INSTRUCTIONS FOR USE

OMVOH™ (ahm-voh)

(mirikizumab-mrkz)

injection, for subcutaneous use

200 mg/2 mL prefilled Pen

This Instructions for Use contains information on how to inject OMVOH.

Before you use the OMVOH prefilled Pen, read and carefully follow all the step-by-step instructions.

Important information you need to know before injecting OMVOH

- For injection under the skin (subcutaneous injection) only.
- Your healthcare provider should show you how to prepare and inject OMVOH using the prefilled Pen. Do not inject yourself or someone else until you have been shown how to inject OMVOH.
- Keep this Instructions for Use and read it as needed.
- The OMVOH prefilled Pen contains 1 full dose of OMVOH. The prefilled Pen is for 1-time use only.
- The OMVOH prefilled Pen contains glass parts. Handle it carefully. If you drop it on a hard surface, do not use it. Use a new OMVOH prefilled Pen for your injection.
- Your healthcare provider may help you decide where on your body to inject your dose. You can also read the Choose and clean your injection site section of these instructions to help you choose which area can work best for you.
- If you have vision or hearing problems, do not use OMVOH prefilled Pen without help from a caregiver.
- See Storing OMVOH for important storage information.

INSTRUCTIONS FOR USE

Before you use the OMVOH prefilled Pen, read and carefully follow all the step-by-step instructions.

Parts of the OMVOH prefilled Pen

Preparing to inject OMVOH
Gather supplies |  |  |  | - OMVOH prefilled Pen from the refrigerator - 1 alcohol wipe - 1 cotton ball or piece of gauze - 1 sharps disposal container
Inspect the prefilled Pen and the medicine |  |  |  | Make sure you have the right medicine. The medicine inside should be clear. It may be colorless to slightly yellow to slightly brown. Do not use the prefilled Pen (see Throwing away (disposing of) OMVOH prefilled Pen) if the:; - prefilled Pen looks damaged - medicine is cloudy, is discolored, or has particles - expiration date printed on the label has passed
Wait 45 minutes |  |  |  | With the gray base cap on, allow the prefilled Pen to warm up to room temperature for 45 minutes before injecting.; - Do not warm up the prefilled Pen with a microwave, hot water, or direct sunlight. - Do not use the prefilled Pen if the medicine has been frozen.
Prepare for injection |  |  |  | Wash your hands with soap and water before you inject OMVOH.
Choose and clean your injection site |  |  |  | Your healthcare provider can help you choose the injection site that is best for you.; - You or another person may inject the medicine into your stomach area (abdomen). Do not inject within 2 inches of the belly button (navel). - You or another person may inject the medicine in the front of your thighs. This area should be at least 2 inches above the knee and 2 inches below the groin. - Another person may give you the injection in the back of your upper arm. - Do not inject in the exact same spot every time. - Do not inject into areas where the skin is tender, bruised, red, or hard.; Clean the injection site with an alcohol wipe. Let the injection site dry before you inject the medicine.
Injecting OMVOH
1 | Uncap the prefilled Pen
1 |  | Make sure the prefilled Pen is locked.
1 | When you are ready to inject, twist off the gray base cap and throw the cap away in your household trash.
1 | Do not put the gray base cap back on. This could damage the needle.
1 | Do not touch the needle inside the clear base.
2 | Place and unlock
2 | Place and hold the clear base flat and firmly against the skin.
 |  |  | Keep the clear base on the skin, then turn the lock ring to the unlock position.

3 | Press and Hold for 15 Seconds
3 | Press and hold the blue injection button and listen for 2 loud clicks:; - First click: injection started - Second click: injection completed
3 | The injection may take up to 15 seconds.
3 | You will know the injection is complete when the gray plunger is visible. Remove the prefilled Pen from the skin. If you have bleeding at the injection site, press a cotton ball or gauze over the injection site. Do not rub the injection site, as this may cause bruising.

Throwing away (disposing of) OMVOH prefilled Pen

Throw away the used prefilled Pen
Put the used OMVOH prefilled Pen in an FDA-cleared sharps disposal container right away after use.
Do not throw away (dispose of) the OMVOH prefilled Pen in the household trash.
For more information, see Used OMVOH prefilled Pen disposal.

Storing OMVOH

Refrigeration

- In the original carton, store your prefilled Pen in the refrigerator between 36°F to 46°F (2°C to 8°C) until the expiration date.
- Do not freeze. Do not use OMVOH if it has been frozen.

Room Temperature

- If needed, your prefilled Pen may be stored at room temperature for up to 2 weeks in the original carton. Do not store above 86°F (30°C).
- When OMVOH has been stored at room temperature, do not return it to the refrigerator.
- Throw away (dispose of) OMVOH if not used within 2 weeks at room temperature.
- Protect your prefilled Pen from light until use.

Do not use the prefilled Pen and throw away (see Throwing away (disposing of) OMVOH prefilled Pen) if it has been:

- frozen
- microwaved
- warmed with hot water
- left in direct sunlight
- shaken

Keep your prefilled Pen and all medicines out of the sight and reach of children.

Commonly Asked Questions
Q. | What if I see bubbles in the prefilled Pen?
A. | Air bubbles are normal. They will not harm you or affect your dose.
Q. | What if I unlock the prefilled Pen and press the blue injection button before twisting off the gray base cap?
A. | Do not remove the gray base cap. Throw away (dispose of) the prefilled Pen and use a new one.
Q. | Do I need to hold the blue injection button down until the injection is complete?
A. | You do not need to hold the blue injection button down, but it may help you keep the prefilled Pen steady and firm against your skin.
Q. | What if the needle did not retract after my injection?
A. | Do not touch the needle or replace the gray base cap. Store the prefilled Pen in a safe place to avoid an accidental needlestick and contact 1-800-Lilly Rx (1-800-545-5979) for instructions on how to return the prefilled Pen.
Q. | What if there is a drop of liquid or blood on my skin after my injection?
A. | This is normal. Press a cotton ball or gauze over the injection site. Do not rub the injection site.
Q. | How can I tell if my injection is complete?
A. | After you press the blue injection button, you will hear 2 loud clicks. The second loud click tells you that your injection is complete. You will also see the gray plunger at the top of the clear base. The injection may take up to 15 seconds.
Q. | What if I remove the prefilled Pen before the second loud click or before the gray plunger stops moving?
A. | You may not have received your full dose. Do not give another injection. Call your healthcare provider for help.
Q. | What if I hear more than 2 clicks during my injection – 2 loud clicks and 1 soft one. Did I get my complete injection?
A. | Some people may hear a soft click right before the second loud click. That is the normal operation of the prefilled Pen. Do not remove the prefilled Pen from your skin until you hear the second loud click.
Q. | How many prefilled Pens do I need to inject in order to get my full dose?
A. | For this medicine, one 2 mL prefilled Pen equals a full dose. If your prescription previously required more injections and you would like to confirm your dose, or you have any questions about your dose, contact your healthcare provider.
Additional Information:
If you have more questions about how to use the OMVOH prefilled Pen:
 | - Call your healthcare provider - Call 1-800-Lilly-Rx (1-800-545-5979) - Visit www.OMVOH.com |  | Scan this code to launch www.OMVOH.com
 | - Call your healthcare provider - Call 1-800-Lilly-Rx (1-800-545-5979) - Visit www.OMVOH.com |  | Scan this code to launch www.OMVOH.com
 | - Call your healthcare provider - Call 1-800-Lilly-Rx (1-800-545-5979) - Visit www.OMVOH.com |  | Scan this code to launch www.OMVOH.com
Used OMVOH prefilled Pen disposal
Put the used OMVOH prefilled Pen in an FDA-cleared sharps disposal container right away after use. Do not throw away (dispose of) the OMVOH prefilled Pen in the household trash.
If you do not have an FDA-cleared sharps disposal container, you may use a household container that is:
- made of a heavy-duty plastic,
- can be closed with a tight-fitting, puncture-resistant lid, without sharps being able to come out,
- upright and stable during use,
- leak-resistant, and
- properly labeled to warn of hazardous waste inside the container.
When your sharps disposal container is almost full, you will need to follow your community guidelines for the right way to dispose of your sharps disposal container.
There may be state or local laws about how you should throw away needles and syringes.
For more information about safe sharps disposal, and for specific information about sharps disposal in the state you live in, go to the FDA's website at http://www.fda.gov/safesharpsdisposal.
Do not recycle your used sharps disposal container.
Read the Medication Guide for OMVOH inside this box to learn more about your medicine.

Manufactured by:
Eli Lilly and Company
Indianapolis, IN 46285, USA
US License Number 1891

OMVOH™ is a trademark of Eli Lilly and Company.

Copyright © 2025, Eli Lilly and Company. All rights reserved.

This Instructions for Use has been approved by the U.S. Food and Drug Administration.

Approved: October 2025

The OMVOH prefilled Pen meets the current dose accuracy and functional requirements of ISO 11608-1 and 11608-5.

OMV-0001-200MG-PEN-IFU-20251023

200 MG PREFILLED SYRINGE INSTRUCTIONS FOR USE

INSTRUCTIONS FOR USE

OMVOH™ (ahm-voh)

(mirikizumab-mrkz)

injection, for subcutaneous use

200 mg/2 mL (100 mg/mL) prefilled Syringe

This Instructions for Use contains information on how to inject OMVOH.

Before you use the OMVOH prefilled Syringe, read and carefully follow all the step-by-step instructions.

Important information you need to know before injecting OMVOH

- For injection under the skin (subcutaneous injection) only.
- Your healthcare provider should show you how to prepare and inject OMVOH using the prefilled Syringe. Do not inject yourself or someone else until you have been shown how to inject OMVOH.
- Keep this Instructions for Use and read it as needed.
- The OMVOH prefilled Syringe contains 1 full dose of OMVOH. The prefilled Syringe is for 1-time use only.
- The OMVOH prefilled Syringe contains glass parts. Handle it carefully. If you drop it on a hard surface, do not use it. Use a new OMVOH prefilled Syringe for your injection.
- Your healthcare provider may help you decide where on your body to inject your dose. You can also read the Choose and clean your injection site section of these instructions to help you choose which area can work best for you.
- If you have vision problems, do not use OMVOH prefilled Syringe without help from a caregiver.
- See Storing OMVOH for important storage information.

INSTRUCTIONS FOR USE

Before you use the OMVOH prefilled Syringe, read and carefully follow all the step-by-step instructions.

Parts of the OMVOH prefilled Syringe

Preparing to inject OMVOH
Gather supplies | - OMVOH prefilled Syringe from the refrigerator - 1 alcohol wipe - 1 cotton ball or piece of gauze - 1 sharps disposal container
Inspect the prefilled Syringe and the medicine | Remove prefilled Syringe from the carton. Make sure you have the right medicine. The medicine inside should be clear. It may be colorless to slightly yellow to slightly brown.
Inspect the prefilled Syringe and the medicine | Do not use the prefilled Syringe (see Throwing away (disposing of) OMVOH prefilled Syringe) if the:; - prefilled Syringe looks damaged - medicine is cloudy, discolored, or has particles - expiration date printed on the label has passed - medicine has been frozen
Wait 45 minutes | Do not warm up the prefilled Syringe with a microwave, hot water, or direct sunlight. With the needle cap on, allow the prefilled Syringe to warm up to room temperature for 45 minutes before injecting.
Prepare for injection | Wash your hands with soap and water before you inject OMVOH.
Choose and clean your injection site | Your healthcare provider can help you choose the injection site that is best for you.; - You or another person may inject the medicine into your stomach area (abdomen). Do not inject within 2 inches of the belly button (navel). - You or another person may inject the medicine in the front of your thighs. This area should be at least 2 inches above the knee and 2 inches below the groin. - Another person may give you the injection in the back of your upper arm. - Do not inject in the exact same spot every time. - Do not inject into areas where the skin is tender, bruised, red, or hard.; Clean the injection site with an alcohol wipe. Let the injection site dry before you inject the medicine.

Injecting OMVOH
1 | Uncap the prefilled Syringe
1 | - Hold the prefilled Syringe body and pull off the needle cap when you are ready to inject. Throw away the needle cap in the household trash.
1 | - Do not put the needle cap back on, this could damage the needle. - Do not touch the needle.
2 | Pinch the injection site and insert the needle
 | - Gently pinch and hold a fold of skin where you will inject. - Insert the needle at a 45-degree angle. - Gently let go of the skin while keeping the needle in place.
 | - Gently pinch and hold a fold of skin where you will inject. - Insert the needle at a 45-degree angle. - Gently let go of the skin while keeping the needle in place.
3 | Inject the medicine
3 | - Slowly push on the thumb pad to push the blue plunger rod all the way in until all the medicine is injected. - The gray Syringe plunger should be pushed all the way to the needle end of the prefilled Syringe.
3 | - You should see the blue plunger rod show through the prefilled Syringe body when the injection is complete as shown. - Remove the needle from your skin. - Do not put the needle cap back on the prefilled Syringe. If you have bleeding at the injection site, press a cotton ball or gauze over the injection site. Do not rub the injection site, as this may cause bruising.

Throwing away (disposing of) OMVOH prefilled Syringe

Throw away the used prefilled Syringe
Put the used OMVOH prefilled Syringe in an FDA-cleared sharps disposal container right away after use.
Do not throw away (dispose of) the OMVOH prefilled Syringe in the household trash.
For more information, see Used OMVOH prefilled Syringe disposal.

Storing OMVOH
Refrigeration

- In the original carton, store your prefilled Syringe in the refrigerator between 36°F to 46°F (2°C to 8°C) until the expiration date.
- Do not freeze. Do not use OMVOH if it has been frozen.

Room Temperature

- If needed, your prefilled Syringe may be stored at room temperature for up to 2 weeks in the original carton. Do not store above 86°F (30°C).
- When OMVOH has been stored at room temperature, do not return it to the refrigerator.
- Throw away (dispose of) OMVOH if not used within 2 weeks at room temperature.
- Protect your prefilled Syringe from light until use.

Do not use the prefilled Syringe and throw away (see Throwing away (disposing of) OMVOH prefilled Syringe) if it has been:

- frozen
- microwaved
- warmed with hot water
- left in direct sunlight
- shaken

Keep your prefilled Syringe and all medicines out of the sight and reach of children.

Commonly Asked Questions

Q.

What if I see air bubbles in the OMVOH prefilled Syringe?

A.

It is normal to have air bubbles in the prefilled Syringe. They will not harm you or affect your dose.

Q.

What if there is a drop of liquid on the tip of the needle when I remove the needle cap?

A.

It is okay to see a drop of liquid on the tip of the needle. This will not harm you or affect your dose.

Q.

What if I cannot push in the plunger?

A.

If the plunger is stuck or damaged:

- Do not continue to use the prefilled Syringe
- Remove the needle from your skin
- Throw away (dispose of) the prefilled Syringe and get a new one

Q.

What if there is a drop of liquid or blood on my skin after my injection?

A.

This is normal. Press a cotton ball or gauze over the injection site. Do not rub the injection site.

Q.

How can I tell if my injection is complete?

A.

When your injection is complete:

- The blue plunger rod should show through the body of the prefilled Syringe.
- The gray Syringe plunger should be pushed all the way to the needle end of the prefilled Syringe.

Q.

How many prefilled Syringes do I need to inject in order to get my full dose?

A.

For this medicine, one 2 mL prefilled Syringe equals a full dose. If your prescription previously required more injections and you would like to confirm your dose, or you have any questions about your dose, contact your healthcare provider.

Additional Information:
If you have more questions about how to use the OMVOH prefilled Syringe:

- Call your healthcare provider
- Call 1-800-Lilly-Rx (1-800-545-5979)
- Visit www.OMVOH.com

Scan this code to launch www.OMVOH.com

Used OMVOH prefilled Syringe disposal
Put the used OMVOH prefilled Syringe in an FDA-cleared sharps disposal container right away after use. Do not throw away (dispose of) the OMVOH prefilled Syringe in the household trash.
If you do not have an FDA-cleared sharps disposal container, you may use a household container that is:

- made of a heavy-duty plastic,
- can be closed with a tight-fitting, puncture-resistant lid, without sharps being able to come out,
- upright and stable during use,
- leak-resistant, and
- properly labeled to warn of hazardous waste inside the container.

When your sharps disposal container is almost full, you will need to follow your community guidelines for the right way to dispose of your sharps disposal container.
There may be state or local laws about how you should throw away needles and syringes.
For more information about safe sharps disposal, and for specific information about sharps disposal in the state you live in, go to the FDA's website at: http://www.fda.gov/safesharpsdisposal.
Do not recycle your used sharps disposal container.

Read the Medication Guide for OMVOH inside this box to learn more about your medicine.

Manufactured by:
Eli Lilly and Company
Indianapolis, IN 46285, USA
US License Number 1891

OMVOH is a trademark of Eli Lilly and Company.

Copyright © 2025, Eli Lilly and Company. All rights reserved.

This Instructions for Use has been approved by the U.S. Food and Drug Administration.

Approved: October 2025

OMV-0001-200MG-PFS-IFU-20251023

PACKAGE LABEL – Omvoh 300 mg Vial Cartons

There are two formulations for this product

NDC 0002-7575-01

15 mL

omvohTM

(mirikizumab-mrkz)

injection

300 mg/15 mL

(20 mg/mL)

For Intravenous Infusion After Dilution

Single-Dose Vial - Discard Unused Portion

Dispense enclosed Medication Guide to each patient.

Rx only

omvoh.com

Lilly

Classic Formulation contains the following inactive ingredients:anhydrous citric acid, polysorbate 80, sodium chloride, sodium citrate, and Water for Injection.

Alternate Formulation contains the following inactive ingredients: anhydrous citric acid, histidine, L-histidine hydrochloride monohydrate, mannitol, polysorbate 80, sodium chloride, sodium citrate, and Water for Injection.

PACKAGE LABEL

PACKAGE LABEL – Omvoh Prefilled Pen 200 mg Dose Carton - Ulcerative Colitis

NDC 0002-8011-27

omvohTM

(mirikizumab-mrkz)
injection

100 mg/mL

For Subcutaneous Use Only

This carton contains a total dose of 200 mg.
Inject both prefilled pens one after the other for a full dose of 200 mg.

Note to Pharmacist: The entire carton is to be dispensed as a unit.

2 x 1 mL single-dose prefilled pens

Rx only

Dispense enclosed Medication Guide to each patient.

Lilly

PACKAGE LABEL

PACKAGE LABEL – Omvoh Prefilled Syringe 200 mg Dose Carton - Ulcerative Colitis

NDC 0002-8870-27

omvohTM

(mirikizumab-mrkz)
injection

100 mg/mL

For Subcutaneous Use Only

Note to Pharmacist: The entire carton is to be dispensed as a unit.

This carton contains a total dose of 200 mg.
Inject both prefilled syringes one after the other for a full dose of 200 mg.

2 x 1 mL single-dose prefilled syringes

Rx only

Dispense enclosed Medication Guide to each patient.

Lilly

PACKAGE LABEL

PACKAGE LABEL – Omvoh Prefilled Pen 300 mg Dose Carton - Crohns Disease

NDC 0002-7717-11

omvohTM

(mirikizumab-mrkz)
injection

200 mg/2 mL
100 mg/mL

For Subcutaneous Use Only

Note to Pharmacist: The entire carton is to be dispensed as a unit.

This carton contains a total dose of 300 mg.
Inject both prefilled pens one after the other for a full dose of 300 mg.

1 x 2 mL single-dose prefilled pen
1 x 1 mL single-dose prefilled pen

Rx only

Dispense enclosed Medication Guide to each patient.

Lilly

PACKAGE LABEL

PACKAGE LABEL – Omvoh Prefilled Syringe 300 mg Dose Carton - Crohns Disease

NDC 0002-7722-11

omvohTM

(mirikizumab-mrkz)
injection

200 mg/2 mL
(100 mg/mL)
100 mg/mL

For Subcutaneous Use Only

Note to Pharmacist: The entire carton is to be dispensed as a unit.

This carton contains a total dose of 300 mg.
Inject both prefilled syringes one after the other for a full dose of 300 mg.

1 x 2 mL single-dose prefilled syringe
1 x 1 mL single-dose prefilled syringe

Rx only

Dispense enclosed Medication Guide to each patient.

Lilly

PACKAGE LABEL

PACKAGE LABEL – Omvoh Prefilled Pen 200 mg Single Injection Dose Carton - Ulcerative Colitis

NDC 0002-3116-11

omvohTM
(mirikizumab-mrkz)
injection

200 mg/2 mL

For Subcutaneous Use Only

This carton contains a total dose of 200 mg.
Only one injection is required for a full dose.

1 x 200mg/2mL single dose prefilled pen

Rx only

Dispense enclosed Medication Guide to each patient.

Lilly

PACKAGE LABEL

PACKAGE LABEL – Omvoh Prefilled Syringe 200 mg Single Injection Dose Carton - Ulcerative Colitis

NDC 0002-1442-11

omvohTM
(mirikizumab-mrkz)
injection

200 mg/2 mL
(100 mg/mL)

For Subcutaneous Use Only

This carton contains a total dose of 200 mg.
Only one injection is required for a full dose.

1 x 200 mg/2 mL single-dose prefilled syringe

Rx only

Dispense enclosed Medication Guide to each patient.

Lilly